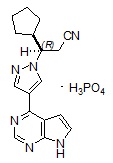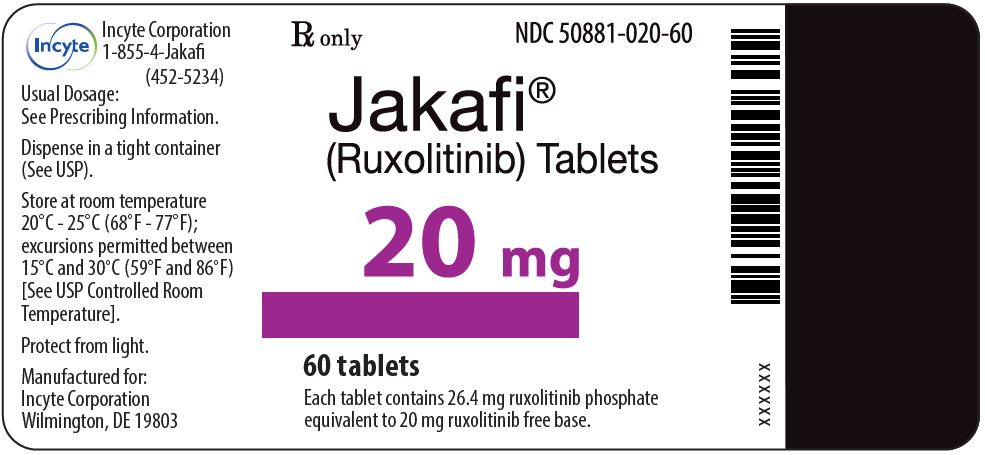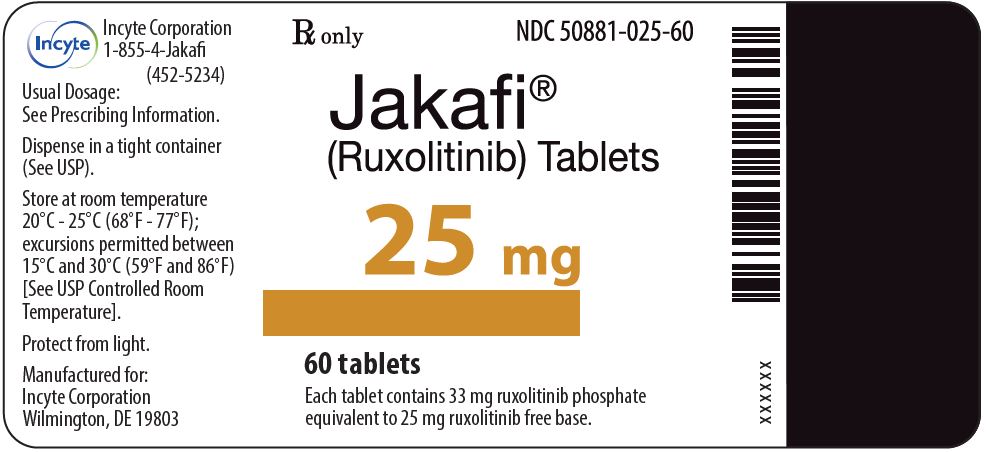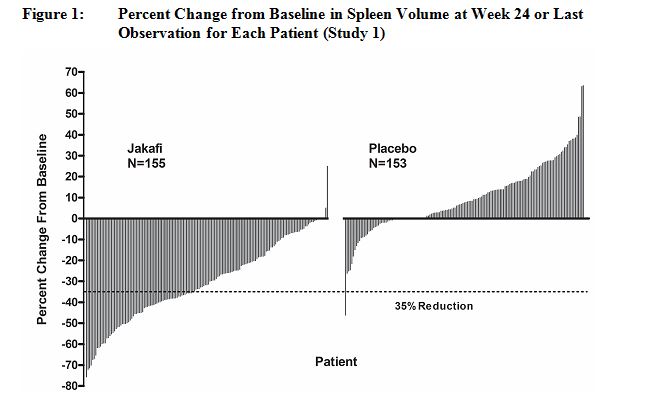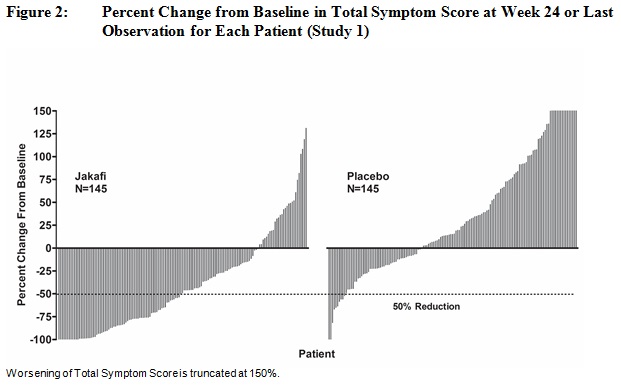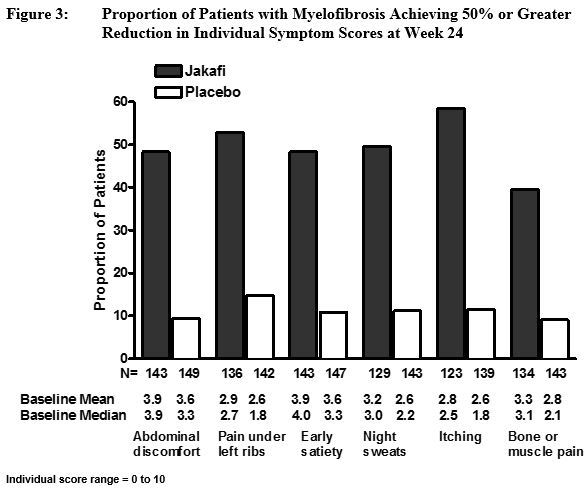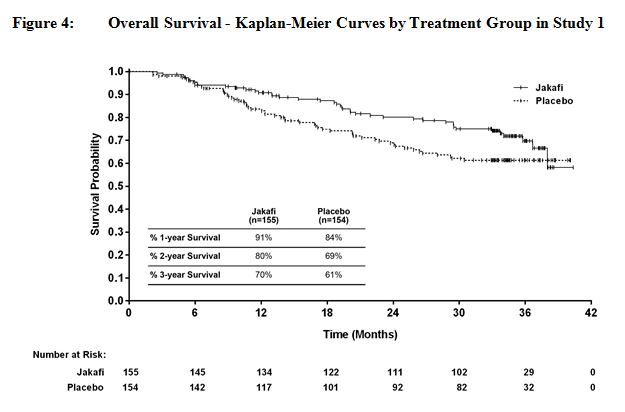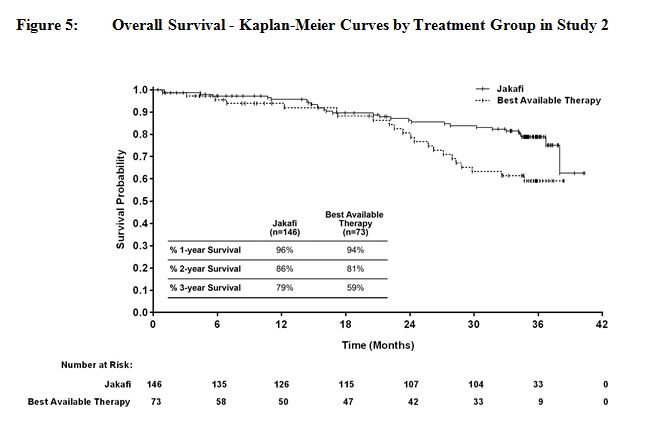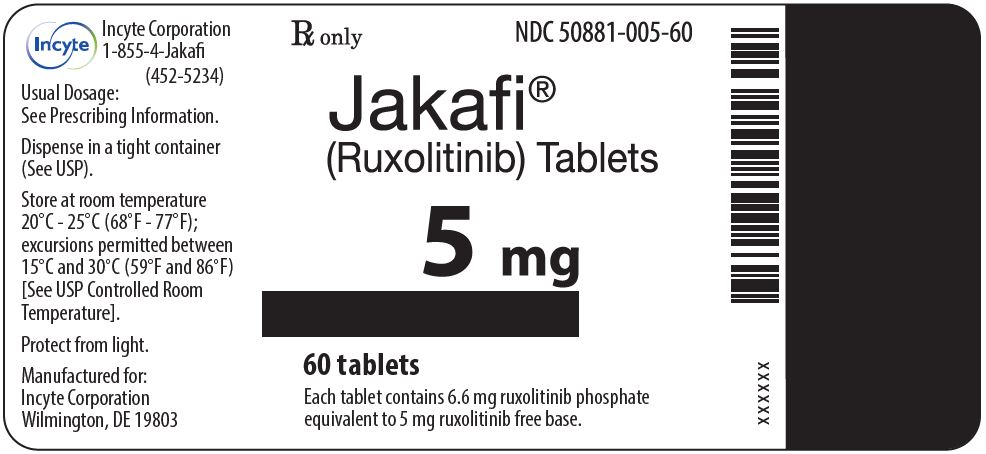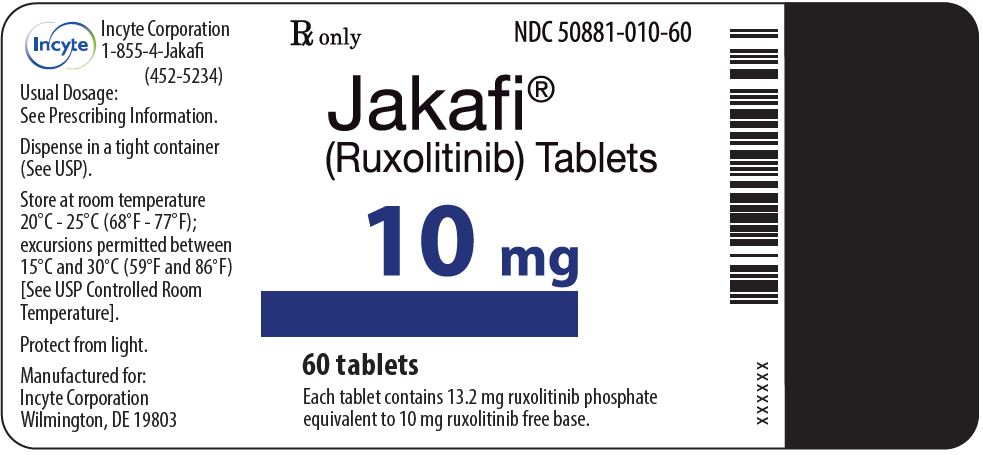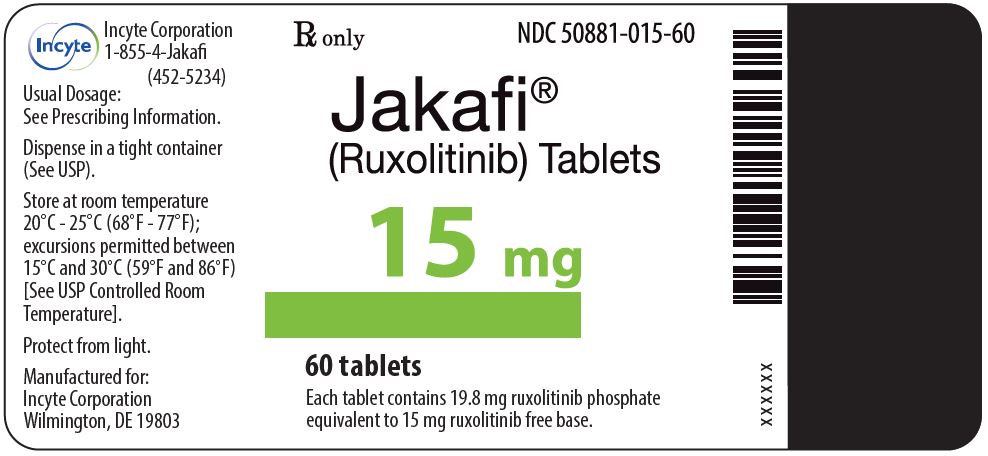 DRUG LABEL: JAKAFI
NDC: 50881-005 | Form: TABLET
Manufacturer: Incyte Corporation
Category: prescription | Type: HUMAN PRESCRIPTION DRUG LABEL
Date: 20250624

ACTIVE INGREDIENTS: RUXOLITINIB 5.0 mg/1 1
INACTIVE INGREDIENTS: CELLULOSE, MICROCRYSTALLINE; LACTOSE MONOHYDRATE; SILICON DIOXIDE; HYDROXYPROPYL CELLULOSE (70000 WAMW); POVIDONE; SODIUM STARCH GLYCOLATE TYPE A POTATO; MAGNESIUM STEARATE

HIGHLIGHTS OF PRESCRIBING INFORMATION

These highlights do not include all the information needed to use JAKAFI safely and effectively. See full prescribing information for JAKAFI.
JAKAFI® (ruxolitinib) tablets, for oral use
Initial U.S. Approval: 2011

RECENT MAJOR CHANGES

Dosage and Administration, Monitoring to Assess Safety (2.1) | 01/2023
Warnings and Precautions, Risk of Infection (5.2) | 01/2023

1. INDICATIONS AND USAGE

Jakafi is a kinase inhibitor indicated for treatment of:

- intermediate or high-risk myelofibrosis, including primary myelofibrosis, post-polycythemia vera myelofibrosis and post-essential thrombocythemia myelofibrosis in adults. (1.1)
- polycythemia vera in adults who have had an inadequate response to or are intolerant of hydroxyurea. (1.2)
- steroid-refractory acute graft-versus-host disease in adult and pediatric patients 12 years and older (1.3)
- chronic graft-versus-host disease after failure of one or two lines of systemic therapy in adult and pediatric patients 12 years and older. (1.4)

2. DOSAGE AND ADMINISTRATION

Doses should be individualized based on safety and efficacy. Starting doses per indication are noted below.

Myelofibrosis (2.2)

- The starting dose of Jakafi is based on patient’s baseline platelet count:
  • Greater than 200 x 10^9/L: 20 mg given orally twice daily
  • 100 x 10^9/L to 200 x 10^9/L: 15 mg given orally twice daily
  • 50 x 10^9/L to less than 100 x 10^9/L: 5 mg given orally twice daily
- Monitor complete blood counts every 2 to 4 weeks until doses are stabilized, and then as clinically indicated. Modify or interrupt dosing for thrombocytopenia.

Polycythemia Vera (2.3)

- The starting dose of Jakafi is 10 mg given orally twice daily.

Acute Graft-Versus-Host Disease (2.4)

- The starting dose of Jakafi is 5 mg given orally twice daily.

Chronic Graft-Versus-Host Disease (2.5)

- The starting dose of Jakafi is 10 mg given orally twice daily.

3. DOSAGE FORMS AND STRENGTHS

Tablets: 5 mg, 10 mg, 15 mg, 20 mg and 25 mg. (3)

4. CONTRAINDICATIONS

None. (4)

5. WARNINGS AND PRECAUTIONS

- Thrombocytopenia, Anemia and Neutropenia: Manage by dose reduction, or interruption, or transfusion. (5.1)
- Risk of Infection: Assess patients for signs and symptoms of infection and initiate appropriate treatment promptly. Serious infections should have resolved before starting therapy with Jakafi. (5.2)
- Symptom Exacerbation Following Interruption or Discontinuation: Manage with supportive care and consider resuming treatment with Jakafi. (5.3)
- Risk of Non-Melanoma Skin Cancer: Perform periodic skin examinations. (5.4)
- Lipid Elevations: Assess lipid levels 8-12 weeks from start of therapy and treat as needed. (5.5)
- Major Adverse Cardiovascular Events (MACE): Monitor for development of MACE. (5.6)
- Thrombosis: Evaluate and treat symptoms of thrombosis promptly. (5.7)
- Secondary Malignancies: Monitor for development of secondary malignancies, particularly in patients who are current or past smokers. (5.8)

6. ADVERSE REACTIONS

- In myelofibrosis and polycythemia vera, the most common hematologic adverse reactions (incidence > 20%) are thrombocytopenia and anemia. The most common nonhematologic adverse reactions (incidence ≥ 15%) are bruising, dizziness, headache, and diarrhea. (6.1)
- In acute graft-versus-host disease, the most common hematologic adverse reactions (incidence > 50%) are anemia, thrombocytopenia, and neutropenia. The most common nonhematologic adverse reactions (incidence > 50%) are infections (pathogen not specified) and edema. (6.1)
- In chronic graft-versus-host disease, the most common hematologic adverse reactions (incidence > 35%) are anemia and thrombocytopenia. The most common nonhematologic adverse reactions (incidence ≥ 20%) are infections (pathogen not specified) and viral infections. (6.1)

To report SUSPECTED ADVERSE REACTIONS, contact Incyte Corporation at 1-855-463-3463 or FDA at 1-800-FDA-1088 or www.fda.gov/medwatch

7. DRUG INTERACTIONS

- Fluconazole: Avoid concomitant use with fluconazole doses greater than 200 mg. Reduce Jakafi dosage with fluconazole doses less than or equal to 200 mg. (2.6, 7)
- Strong CYP3A4 Inhibitors: Reduce, interrupt, or discontinue Jakafi doses as recommended except in patients with acute or chronic graft-versus-host-disease. (2.6, 7)

8. USE IN SPECIFIC POPULATIONS

- Renal Impairment: Reduce Jakafi starting dose or avoid treatment as recommended. (2.7, 8.6)
- Hepatic Impairment: Reduce Jakafi starting dose or avoid treatment as recommended. (2.7, 8.7)
- Lactation: Advise not to breastfeed. (8.2)

FULL PRESCRIBING INFORMATION

RECENT MAJOR CHANGES

kjhkj | bnvv

1. INDICATIONS AND USAGE

1.1 Myelofibrosis

Jakafi is indicated for treatment of intermediate or high-risk myelofibrosis (MF), including primary MF, post-polycythemia vera MF and post-essential thrombocythemia MF in adults.

1.2 Polycythemia Vera

Jakafi is indicated for treatment of polycythemia vera (PV) in adults who have had an inadequate response to or are intolerant of hydroxyurea.

1.3 Acute Graft-Versus-Host Disease

Jakafi is indicated for treatment of steroid-refractory acute graft-versus-host disease (aGVHD) in adult and pediatric patients 12 years and older.

1.4 Chronic Graft-Versus-Host Disease

Jakafi is indicated for treatment of chronic graft-versus-host disease (cGVHD) after failure of one or two lines of systemic therapy in adult and pediatric patients 12 years and older.

2. DOSAGE AND ADMINISTRATION

2.1 Monitoring to Assess Safety

Prior to Jakafi treatment:

- Perform a complete blood count [see Warnings and Precautions (5.1)].
- Inquire about past infections, including tuberculosis, herpes simplex, herpes zoster, and hepatitis B [see Warnings and Precautions (5.2)].

During treatment with Jakafi:

- Perform a complete blood count every 2 to 4 weeks until doses are stabilized, and then as clinically indicated [see Warnings and Precautions (5.1)].
- Assess lipid parameters approximately 8-12 weeks following initiation of Jakafi therapy [see Warnings and Precautions (5.5)].

2.2 Recommended Dosage for Myelofibrosis

The recommended starting dose of Jakafi is based on platelet count (Table 1). Doses may be titrated based on safety and efficacy.

Table 1: Jakafi Starting Doses for Myelofibrosis
Platelet Count | Starting Dose
Greater than 200 x 10^9/L | 20 mg orally twice daily
100 x 10^9/L to 200 x 10^9/L | 15 mg orally twice daily
50 x 10^9/L to less than 100 x 10^9/L | 5 mg orally twice daily

Dose Modification Guidelines for Hematologic Toxicity for Patients with Myelofibrosis Starting Treatment with a Platelet Count of 100 x 10^9/L or Greater

Treatment Interruption and Restarting Dosing

Interrupt treatment for platelet counts less than 50 x 10^9/L or absolute neutrophil count (ANC) less than 0.5 x 10^9/L.

After recovery of platelet counts above 50 x 10^9/L and ANC above 0.75 x 10^9/L, dosing may be restarted. Table 2 illustrates the maximum allowable dose that may be used in restarting Jakafi after a previous interruption.

Table 2: Myelofibrosis: Maximum Restarting Doses for Jakafi after Safety Interruption for Thrombocytopenia for Patients Starting Treatment with a Platelet Count of 100 x 10^9/L or Greater
Current Platelet Count | Maximum Dose When Restarting Jakafi Treatment [Maximum doses are displayed. When restarting, begin with a dose at least 5 mg twice daily below the dose at interruption.]
Greater than or equal to 125 x 10^9/L | 20 mg twice daily
100 to less than 125 x 10^9/L | 15 mg twice daily
75 to less than 100 x 10^9/L | 10 mg twice daily for at least 2 weeks; if stable, may increase to 15 mg twice daily
50 to less than 75 x 10^9/L | 5 mg twice daily for at least 2 weeks; if stable, may increase to 10 mg twice daily
Less than 50 x 10^9/L | Continue hold

Following treatment interruption for ANC below 0.5 x 10^9/L, after ANC recovers to 0.75 x 10^9/L or greater, restart dosing at the higher of 5 mg once daily or 5 mg twice daily below the largest dose in the week prior to the treatment interruption.

Dose Reductions
Dose reductions should be considered if the platelet counts decrease as outlined in Table 3 with the goal of avoiding dose interruptions for thrombocytopenia.

Table 3: Myelofibrosis: Dosing Recommendations for Thrombocytopenia for Patients Starting Treatment with a Platelet Count of 100 x 10^9/L or Greater
 | Dose at Time of Platelet Decline
Platelet Count | 25 mg twice daily | 20 mg twice daily | 15 mg twice daily | 10 mg twice daily | 5 mg twice daily
Platelet Count | New Dose | New Dose | New Dose | New Dose | New Dose
100 to less than 125 x 10^9/L | 20 mg twice daily | 15 mg twice daily | No Change | No Change | No Change
75 to less than 100 x 10^9/L | 10 mg twice daily | 10 mg twice daily | 10 mg twice daily | No Change | No Change
50 to less than 75 x 10^9/L | 5 mg twice daily | 5 mg twice daily | 5 mg twice daily | 5 mg twice daily | No Change
Less than 50 x 10^9/L | Hold | Hold | Hold | Hold | Hold

Dose Modification Based on Insufficient Response for Patients with Myelofibrosis Starting Treatment with a Platelet Count of 100 x 10^9/L or Greater

If the response is insufficient and platelet and neutrophil counts are adequate, doses may be increased in 5 mg twice daily increments to a maximum of 25 mg twice daily. Doses should not be increased during the first 4 weeks of therapy and not more frequently than every 2 weeks.

Consider dose increases in patients who meet all of the following conditions:

1. Failure to achieve a reduction from pretreatment baseline in either palpable spleen length of 50% or a 35% reduction in spleen volume as measured by computed tomography (CT) or magnetic resonance imaging (MRI);
2. Platelet count greater than 125 x 10^9/L at 4 weeks and platelet count never below 100 x 10^9/L;
3. ANC Levels greater than 0.75 x 10^9/L.

Based on limited clinical data, long-term maintenance at a 5 mg twice daily dose has not shown responses and continued use at this dose should be limited to patients in whom the benefits outweigh the potential risks. Discontinue Jakafi if there is no spleen size reduction or symptom improvement after 6 months of therapy.

Dose Modifications for Hematologic Toxicity for Patients with Myelofibrosis Starting Treatment with Platelet Counts of 50 x 10^9/L to Less Than 100 x 10^9/L

This section applies only to patients with platelet counts of 50 x 10^9/L to less than 100 x 10^9/L prior to any treatment with Jakafi. See dose modifications in Section 2.2 (Dose Modification Guidelines for Hematological Toxicity for Patients with Myelofibrosis Starting Treatment with a Platelet Count of 100 x 10^9/L or Greater) for hematological toxicity in patients whose platelet counts were 100 x 10^9/L or more prior to starting treatment with Jakafi.

Treatment Interruption and Restarting Dosing

Interrupt treatment for platelet counts less than 25 x 10^9/L or ANC less than 0.5 x 10^9/L.

After recovery of platelet counts above 35 x 10^9/L and ANC above 0.75 x 10^9/L, dosing may be restarted. Restart dosing at the higher of 5 mg once daily or 5 mg twice daily below the largest dose in the week prior to the decrease in platelet count below 25 x 10^9/L or ANC below 0.5 x 10^9/L that led to dose interruption.

Dose Reductions

Reduce the dose of Jakafi for platelet counts less than 35 x 10^9/L as described in Table 4.

Table 4: Myelofibrosis: Dosing Modifications for Thrombocytopenia for Patients with Starting Platelet Count of 50 x 10^9/L to Less Than 100 x 10^9/L
Platelet Count | Dosing Recommendations
Less than 25 x 10^9/L | - Interrupt dosing.
25 x 10^9/L to less than 35 x 10^9/L AND the platelet count decline is less than 20% during the prior four weeks | - Decrease dose by 5 mg once daily. - For patients on 5 mg once daily, maintain dose at 5 mg once daily.
25 x 10^9/L to less than 35 x 10^9/L AND the platelet count decline is 20% or greater during the prior four weeks | - Decrease dose by 5 mg twice daily. - For patients on 5 mg twice daily, decrease the dose to 5 mg once daily. - For patients on 5 mg once daily, maintain dose at 5 mg once daily.

Dose Modifications Based on Insufficient Response for Patients with Myelofibrosis and Starting Platelet Count of 50 x 10^9/L to Less Than 100 x 10^9/L

Do not increase doses during the first 4 weeks of therapy, and do not increase the dose more frequently than every 2 weeks.

If the response is insufficient as defined in Section 2.2 (see Dose Modification Based on Insufficient Response with Myelofibrosis Starting Treatment with a platelet count of 100 x 10^9/L or Greater), doses may be increased by increments of 5 mg daily to a maximum of 10 mg twice daily if:

1. the platelet count has remained at least 40 x 10^9/L, and
2. the platelet count has not fallen by more than 20% in the prior 4 weeks, and
3. the ANC is more than 1 x 10^9/L, and
4. the dose has not been reduced or interrupted for an adverse event or hematological toxicity in the prior 4 weeks.

Continuation of treatment for more than 6 months should be limited to patients in whom the benefits outweigh the potential risks. Discontinue Jakafi if there is no spleen size reduction or symptom improvement after 6 months of therapy.

Dose Modification for Bleeding

Interrupt treatment for bleeding requiring intervention regardless of current platelet count. Once the bleeding event has resolved, consider resuming treatment at the prior dose if the underlying cause of bleeding has been controlled. If the bleeding event has resolved but the underlying cause persists, consider resuming treatment with Jakafi at a lower dose.

2.3 Recommended Dosage for Polycythemia Vera

The recommended starting dose of Jakafi is 10 mg twice daily. Doses may be titrated based on safety and efficacy.

Dose Modification Guidelines for Patients with Polycythemia Vera

Dose Reductions

Dose reductions should be considered for hemoglobin and platelet count decreases as described in Table 5.

Table 5: Polycythemia Vera: Dose Reductions
Hemoglobin and/or Platelet Count | Dosing Recommendations
Hemoglobin greater than or equal to 12 g/dL AND platelet count greater than or equal to 100 x 10^9/L | - No change required.
Hemoglobin 10 to less than 12 g/dL AND platelet count 75 to less than 100 x 10^9/L | - Dose reductions should be considered with the goal of avoiding dose interruptions for anemia and thrombocytopenia.
Hemoglobin 8 to less than 10 g/dL OR platelet count 50 to less than 75 x 10^9/L | - Reduce dose by 5 mg twice daily. - For patients on 5 mg twice daily, decrease the dose to 5 mg once daily.
Hemoglobin less than 8 g/dL OR platelet count less than 50 x 10^9/L | - Interrupt dosing.

Treatment Interruption and Restarting Dosing

Interrupt treatment for hemoglobin less than 8 g/dL, platelet counts less than 50 x 10^9/L or ANC less than 1.0 x 10^9/L.

After recovery of the hematologic parameter(s) to acceptable levels, dosing may be restarted.

Table 6 illustrates the dose that may be used in restarting Jakafi after a previous interruption.

Table 6: Polycythemia Vera: Restarting Doses for Jakafi after Safety Interruption for Hematologic Parameter(s)

Use the most severe category of a patient’s hemoglobin, platelet count, or ANC abnormality to determine the corresponding maximum restarting dose.

Hemoglobin, Platelet Count, or ANC | Maximum Restarting Dose
Hemoglobin less than 8 g/dL OR platelet count less than 50 x 10^9/L OR ANC less than 1 x 10^9/L | Continue hold
Hemoglobin 8 to less than 10 g/dL OR platelet count 50 to less than 75 x 10^9/L OR ANC 1 to less than 1.5 x 10^9/L | 5 mg twice daily [Continue treatment for at least 2 weeks; if stable, may increase dose by 5 mg twice daily.] or no more than 5 mg twice daily less than the dose which resulted in dose interruption
Hemoglobin 10 to less than 12 g/dL OR platelet count 75 to less than 100 x 10^9/L OR ANC 1.5 to less than 2 x 10^9/L | 10 mg twice dailyor no more than 5 mg twice daily less than the dose which resulted in dose interruption
Hemoglobin greater than or equal to 12 g/dL OR platelet count greater than or equal to 100 x 10^9/L OR ANC greater than or equal to 2 x 10^9/L | 15 mg twice dailyor no more than 5 mg twice daily less than the dose which resulted in dose interruption

Patients who had required dose interruption while receiving a dose of 5 mg twice daily, may restart at a dose of 5 mg twice daily or 5 mg once daily, but not higher, once hemoglobin is greater than or equal to 10 g/dL, platelet count is greater than or equal to 75 x 10^9/L, and ANC is greater than or equal to 1.5 x 10^9/L.

Dose Management after Restarting Treatment

After restarting Jakafi following treatment interruption, doses may be titrated, but the maximum total daily dose should not exceed 5 mg less than the dose that resulted in the dose interruption. An exception to this is dose interruption following phlebotomy-associated anemia, in which case the maximal total daily dose allowed after restarting Jakafi would not be limited.

Dose Modifications Based on Insufficient Response for Patients with Polycythemia Vera

If the response is insufficient and platelet, hemoglobin, and neutrophil counts are adequate, doses may be increased in 5 mg twice daily increments to a maximum of 25 mg twice daily. Doses should not be increased during the first 4 weeks of therapy and not more frequently than every two weeks.

Consider dose increases in patients who meet all of the following conditions:

1. Inadequate efficacy as demonstrated by one or more of the following:
  1. Continued need for phlebotomy
  2. WBC greater than the upper limit of normal range
  3. Platelet count greater than the upper limit of normal range
  4. Palpable spleen that is reduced by less than 25% from Baseline
2. Platelet count greater than or equal to 140 x 10^9/L
3. Hemoglobin greater than or equal to 12 g/dL
4. ANC greater than or equal to 1.5 x 10^9/L

2.4 Recommended Dosage for Acute Graft-Versus-Host Disease

The recommended starting dose of Jakafi is 5 mg given orally twice daily. Consider increasing the dose to 10 mg twice daily after at least 3 days of treatment if the ANC and platelet counts are not decreased by 50% or more relative to the first day of dosing with Jakafi.

Consider tapering Jakafi after 6 months of treatment in patients with response who have discontinued therapeutic doses of corticosteroids. Taper Jakafi by one dose level approximately every 8 weeks (10 mg twice daily to 5 mg twice daily to 5 mg once daily). If aGVHD signs or symptoms recur during or after the taper of Jakafi, consider retreatment.

Dose Modification Guidelines for Patients with Acute Graft-Versus-Host Disease

Monitor complete blood counts (CBC), including platelet count and ANC, and bilirubin prior to initiating therapy, every 2 to 4 weeks until doses are stabilized, and then as indicated clinically.

Modify the dose of Jakafi for adverse reactions as described in Table 7. For dose reductions, patients who are currently receiving Jakafi 10 mg twice daily may have their dose reduced to 5 mg twice daily; patients receiving 5 mg twice daily may have their dose reduced to 5 mg once daily. Patients who are unable to tolerate Jakafi at a dose of 5 mg once daily should have treatment interrupted until their clinical and/or laboratory parameters recover.

Table 7: Dose Modifications for Adverse Reactions in Patients with Acute GVHD
Laboratory Parameter | Dosing Recommendations
Clinically significant thrombocytopenia after supportive measures | Reduce dose by 1 dose level. When platelets recover to previous values, dosing may return to prior dose level.
ANC less than 1 x 10^9/L considered related to Jakafi | Hold Jakafi for up to 14 days; resume at 1 dose level lower upon recovery.
Total Bilirubin elevation, no liver GVHD | 3.0−5.0 x ULN: Continue Jakafi at 1 dose level lower until recovery.; > 5.0−10.0 x ULN: Hold Jakafi for up to 14 days until bilirubin ≤ 1.5 x ULN; resume at current dose upon recovery.; Total bilirubin > 10.0 x ULN: Hold Jakafi for up to 14 days until bilirubin ≤ 1.5 x ULN; resume at 1 dose level lower upon recovery.
Total Bilirubin elevation, liver GVHD | > 3.0 × ULN: Continue Jakafi at 1 dose level lower until recovery.

2.5 Recommended Dosage for Chronic Graft-Versus-Host Disease

The recommended starting dose of Jakafi is 10 mg given orally twice daily.

Consider tapering Jakafi after 6 months of treatment in patients with response who have discontinued therapeutic doses of corticosteroids. Taper Jakafi by one dose level approximately every 8 weeks (10 mg twice daily to 5 mg twice daily to 5 mg once daily). If GVHD signs or symptoms recur during or after the taper of Jakafi, consider retreatment.

Dose Modification Guidelines for Patients with Chronic Graft-Versus-Host Disease

Monitor complete blood counts (CBC), including platelet count and ANC, and bilirubin prior to initiating therapy, every 2 to 4 weeks until doses are stabilized, and then as indicated clinically.

Modify the dose of Jakafi for adverse reactions as described in Table 8. For dose reductions, patients who are currently receiving Jakafi 10 mg twice daily may have their dose reduced to 5 mg twice daily; patients receiving 5 mg twice daily may have their dose reduced to 5 mg once daily. Patients who are unable to tolerate Jakafi at a dose of 5 mg once daily should have treatment interrupted until their clinical and/or laboratory parameters recover.

Table 8: Dose Modifications for Adverse Reactions in Patients with Chronic GVHD
Parameter | Dosing Recommendations
Platelet count less than 20 × 10^9/L | Reduce Jakafi by 1 dose level. If resolved within 7 days, dosing may return to initial dose level. If not resolved within 7 days, then maintain at 1 dose level lower.
ANC less than 0.75 × 10^9/L considered related to Jakafi | Reduce Jakafi by 1 dose level; resume at initial dose level upon recovery.
ANC less than 0.5 × 10^9/L considered related to Jakafi | Hold Jakafi for up to 14 days; resume at 1 dose level lower upon recovery. May resume initial dose level when ANC greater than 1.0 × 10^9/L.
Total Bilirubin: 3.0-5.0 × ULN | Continue Jakafi at 1 dose level lower until recovery. If resolved within 14 days, then increase by one dose level. If not resolved within 14 days, then maintain the decreased dose level.
Total Bilirubin: > 5.0-10.0 × ULN | Hold Jakafi for up to 14 days until resolved; resume at current dose upon recovery. If not resolved within 14 days, then resume at 1 dose level lower upon recovery.
Total Bilirubin: > 10.0 × ULN | Hold Jakafi for up to 14 days until resolved; resume at 1 dose level lower upon recovery. If not resolved within 14 days, discontinue.
Other Adverse Reactions: Grade 3 | Continue Jakafi at 1 dose level lower until recovery.
Other Adverse Reactions: Grade 4 | Discontinue Jakafi.

2.6 Dose Modifications for Concomitant Use with Strong CYP3A4 Inhibitors or Fluconazole

Modify the Jakafi dosage when coadministered with strong CYP3A4 inhibitors or doses of less than or equal to 200 mg of fluconazole [see Drug Interactions (7)], according to Table 9. Avoid concomitant use of Jakafi with fluconazole doses of greater than 200 mg daily.

Table 9: Dose Modifications for Concomitant Use with Strong CYP3A4 Inhibitors or Fluconazole
For patients coadministered strong CYP3A4 inhibitors or doses of less than or equal to 200 mg of fluconazole | Recommended Jakafi Dose Modification
Starting dose for patients with MF with a platelet count:
- Greater than or equal to 100 x 10^9/L | 10 mg twice daily
- 50 x 10^9/L to less than 100 x 10^9/L | 5 mg once daily
Starting dose for patients with PV: | 5 mg twice daily
If on stable dose for patients with MF or PV:
- Greater than or equal to 10 mg twice daily | Decrease dose by 50% (round up to the closest available tablet strength)
- 5 mg twice daily | 5 mg once daily
- 5 mg once daily | Avoid strong CYP3A4 inhibitor or fluconazole treatment or interrupt Jakafi treatment for the duration of strong CYP3A4 inhibitor or fluconazole use
Starting dosefor patients with aGVHD or cGVHD:
Fluconazole doses of less than or equal to 200 mg | 5 mg once daily for patients with aGVHD; 5 mg twice daily for patients with cGVHD
Other CYP3A4 inhibitors | Monitor blood counts more frequently for toxicity and modify the Jakafi dosage for adverse reactions if they occur [see Dosage and Administration (2.4, 2.5)].

2.7 Dose Modifications for Renal or Hepatic Impairment

Moderate to Severe Renal Impairment or End Stage Renal Disease on Dialysis

Modify the Jakafi dosage for patients with moderate (CLcr 30 to 59 mL/min) to severe (CLcr 15 to 29 mL/min) renal impairment or end stage renal disease (ESRD) on dialysis according to Table 10. Avoid use of Jakafi in patients with ESRD (CLcr less than 15 mL/min) not requiring dialysis [see Use in Specific Populations (8.6)].

Table 10: Dose Modifications for Renal Impairment
Renal Impairment Status | Platelet Count | Recommended Starting Dosage
Patients with MF
Moderate or Severe | Greater than 150 x 10^9/L | No dose adjustment
Moderate or Severe | 100 to 150 x 10^9/L | 10 mg twice daily
Moderate or Severe | 50 to less than 100 x 10^9/L | 5 mg daily
Moderate or Severe | Less than 50 x 10^9/L | Avoid use [see Use in Specific Populations (8.6)]
ESRD on dialysis | 100 to 200 x 10^9/L | 15 mg once after dialysis session
ESRD on dialysis | Greater than 200 x 10^9/L | 20 mg once after dialysis session
Patients with PV
Moderate or Severe | Any | 5 mg twice daily
ESRD on dialysis | Any | 10 mg once after dialysis session
Patients with aGVHD
Moderate or Severe | Any | 5 mg once daily
ESRD on dialysis | Any | 5 mg once after dialysis session
Patients with cGVHD
Moderate or Severe | Any | 5 mg twice daily
ESRD on dialysis | Any | 10 mg once after dialysis session
ESRD = end stage renal disease, and CLcr = creatinine clearance

Hepatic Impairment

Modify the Jakafi dosage for patients with hepatic impairment according to Table 11.

Table 11: Dose Modifications for Hepatic Impairment
Hepatic Impairment Status | Platelet Count | Recommended Starting Dosage
Patients with MF Mild, Moderate, or Severe (Child-Pugh Class A, B, C) | Greater than 150 x 10^9/L | No dose adjustment
Patients with MF Mild, Moderate, or Severe (Child-Pugh Class A, B, C) | 100 x 10^9/L to 150 x 10^9/L | 10 mg twice daily
Patients with MF Mild, Moderate, or Severe (Child-Pugh Class A, B, C) | 50 to less than 100 x 10^9/L | 5 mg daily
Patients with MF Mild, Moderate, or Severe (Child-Pugh Class A, B, C) | Less than 50 x 10^9/L | Avoid use [see Use in Specific Populations (8.7)]
Patients with PV Mild, Moderate, or Severe (Child-Pugh Class A, B, C) | Any | 5 mg twice daily
Patients with aGVHD
Mild, Moderate, or Severe based on NCI criteria without liver GVHD | Any | No dose adjustment
Stage 1, 2 or 3 Liver aGVHD | Any | No dose adjustment
Stage 4 Liver aGVHD | Any | 5 mg once daily
Patients with cGVHD
Mild, Moderate, or Severe based on NCI criteria without liver GVHD | Any | No dose adjustment
Score 1 or 2 Liver cGVHD | Any | No dose adjustment
Score 3 Liver cGVHD | Any | Monitor blood counts more frequently for toxicity and modify the Jakafi dosage for adverse reactions if they occur [see Dosage and Administration (2.4, 2.5)].

2.8 Method of Administration

Jakafi is dosed orally and can be administered with or without food.

If a dose is missed, the patient should not take an additional dose, but should take the next usual prescribed dose.

When discontinuing Jakafi therapy for reasons other than thrombocytopenia, gradual tapering of the dose of Jakafi may be considered, for example by 5 mg twice daily each week.

For patients unable to ingest tablets, Jakafi can be administered through a nasogastric tube (8 French or greater) as follows:

- Suspend one tablet in approximately 40 mL of water with stirring for approximately 10 minutes.
- Within 6 hours after the tablet has dispersed, the suspension can be administered through a nasogastric tube using an appropriate syringe.

The tube should be rinsed with approximately 75 mL of water. The effect of tube feeding preparations on Jakafi exposure during administration through a nasogastric tube has not been evaluated.

3. DOSAGE FORMS AND STRENGTHS

5 mg tablets - round and white with "INCY" on one side and "5" on the other.

10 mg tablets - round and white with "INCY" on one side and "10" on the other.

15 mg tablets - oval and white with "INCY" on one side and "15" on the other.

20 mg tablets - capsule-shaped and white with "INCY" on one side and "20" on the other.

25 mg tablets - oval and white with "INCY" on one side and "25" on the other.

4. CONTRAINDICATIONS

None.

5. WARNINGS AND PRECAUTIONS

5.1 Thrombocytopenia, Anemia and Neutropenia

Treatment with Jakafi can cause thrombocytopenia, anemia and neutropenia [see Adverse Reactions (6.1)].

Manage thrombocytopenia by reducing the dose or temporarily interrupting Jakafi. Platelet transfusions may be necessary [see Dosage and Administration (2)].

Patients developing anemia may require blood transfusions and/or dose modifications of Jakafi.

Severe neutropenia (ANC less than 0.5 × 10^9/L) was generally reversible by withholding Jakafi until recovery.

Perform a pre-treatment complete blood count (CBC) and monitor CBCs every 2 to 4 weeks until doses are stabilized, and then as clinically indicated [see Dosage and Administration (2)].

5.2 Risk of Infection

Serious bacterial, mycobacterial, fungal and viral infections have occurred [see Adverse Reactions (6.1)]. Delay starting therapy with Jakafi until active serious infections have resolved. Observe patients receiving Jakafi for signs and symptoms of infection and manage promptly. Use active surveillance and prophylactic antibiotics according to clinical guidelines.

Tuberculosis

Tuberculosis infection has been reported in patients receiving Jakafi. Observe patients receiving Jakafi for signs and symptoms of active tuberculosis and manage promptly.

Prior to initiating Jakafi, patients should be evaluated for tuberculosis risk factors, and those at higher risk should be tested for latent infection. Risk factors include, but are not limited to, prior residence in or travel to countries with a high prevalence of tuberculosis, close contact with a person with active tuberculosis, and a history of active or latent tuberculosis where an adequate course of treatment cannot be confirmed.

For patients with evidence of active or latent tuberculosis, consult a physician with expertise in the treatment of tuberculosis before starting Jakafi. The decision to continue Jakafi during treatment of active tuberculosis should be based on the overall risk-benefit determination.

Progressive Multifocal Leukoencephalopathy

Progressive multifocal leukoencephalopathy (PML) has occurred with Jakafi treatment. If PML is suspected, stop Jakafi and evaluate.

Herpes Zoster and Herpes Simplex

Herpes zoster infection has been reported in patients receiving Jakafi [see Adverse Reactions (6.1)]. Advise patients about early signs and symptoms of herpes zoster and to seek treatment as early as possible if suspected.

Herpes simplex virus reactivation and/or dissemination has been reported in patients receiving Jakafi [see Adverse Reactions (6.2)]. Monitor patients for the development of herpes simplex infections. If a patient develops evidence of dissemination of herpes simplex, consider interrupting treatment with Jakafi; patients should be promptly treated and monitored according to clinical guidelines.

Hepatitis B

Hepatitis B viral load (HBV-DNA titer) increases, with or without associated elevations in alanine aminotransferase and aspartate aminotransferase, have been reported in patients with chronic HBV infections taking Jakafi. The effect of Jakafi on viral replication in patients with chronic HBV infection is unknown. Patients with chronic HBV infection should be treated and monitored according to clinical guidelines.

5.3 Symptom Exacerbation Following Interruption or Discontinuation of Treatment with Jakafi

Following discontinuation of Jakafi, symptoms from myeloproliferative neoplasms may return to pretreatment levels over a period of approximately one week. Some patients with MF have experienced one or more of the following adverse events after discontinuing Jakafi: fever, respiratory distress, hypotension, DIC, or multi-organ failure. If one or more of these occur after discontinuation of, or while tapering the dose of Jakafi, evaluate for and treat any intercurrent illness and consider restarting or increasing the dose of Jakafi. Instruct patients not to interrupt or discontinue Jakafi therapy without consulting their physician. When discontinuing or interrupting therapy with Jakafi for reasons other than thrombocytopenia or neutropenia [see Dosage and Administration (2.8)], consider tapering the dose of Jakafi gradually rather than discontinuing abruptly.

5.4 Non-Melanoma Skin Cancer (NMSC)

Non-melanoma skin cancers including basal cell, squamous cell, and Merkel cell carcinoma have occurred in patients treated with Jakafi. Perform periodic skin examinations.

5.5 Lipid Elevations

Treatment with Jakafi has been associated with increases in lipid parameters including total cholesterol, low-density lipoprotein (LDL) cholesterol, and triglycerides [see Adverse Reactions (6.1)]. The effect of these lipid parameter elevations on cardiovascular morbidity and mortality has not been determined in patients treated with Jakafi. Assess lipid parameters approximately 8-12 weeks following initiation of Jakafi therapy. Monitor and treat according to clinical guidelines for the management of hyperlipidemia.

5.6 Major Adverse Cardiovascular Events (MACE)

Another JAK-inhibitor has increased the risk of MACE, including cardiovascular death, myocardial infarction, and stroke (compared to those treated with TNF blockers) in patients with rheumatoid arthritis, a condition for which Jakafi is not indicated.

Consider the benefits and risks for the individual patient prior to initiating or continuing therapy with Jakafi particularly in patients who are current or past smokers and patients with other cardiovascular risk factors. Patients should be informed about the symptoms of serious cardiovascular events and the steps to take if they occur.

5.7 Thrombosis

Another JAK-inhibitor has increased the risk of thrombosis, including deep venous thrombosis (DVT), pulmonary embolism (PE), and arterial thrombosis (compared to those treated with TNF blockers) in patients with rheumatoid arthritis, a condition for which Jakafi is not indicated. In patients with MF and PV treated with Jakafi in clinical trials, the rates of thromboembolic events were similar in Jakafi and control treated patients.

Patients with symptoms of thrombosis should be promptly evaluated and treated appropriately.

5.8 Secondary Malignancies

Another JAK-inhibitor has increased the risk of lymphoma and other malignancies excluding NMSC (compared to those treated with TNF blockers) in patients with rheumatoid arthritis, a condition for which Jakafi is not indicated. Patients who are current or past smokers are at additional increased risk.

Consider the benefits and risks for the individual patient prior to initiating or continuing therapy with Jakafi, particularly in patients with a known secondary malignancy (other than a successfully treated NMSC), patients who develop a malignancy, and patients who are current or past smokers.

6. ADVERSE REACTIONS

The following clinically significant adverse reactions are discussed in greater detail in other sections of the labeling:

- Thrombocytopenia, Anemia and Neutropenia [see Warnings and Precautions (5.1)]
- Risk of Infection [see Warnings and Precautions (5.2)]
- Symptom Exacerbation Following Interruption or Discontinuation of Treatment with Jakafi [see Warnings and Precautions (5.3)]
- Non-Melanoma Skin Cancer [see Warnings and Precautions (5.4)]
- Lipid Elevations [see Warnings and Precautions (5.5)]
- Major Adverse Cardiovascular Events (MACE) [see Warnings and Precautions (5.6)]
- Thrombosis [see Warnings and Precautions (5.7)]
- Secondary Malignancies [see Warnings and Precautions (5.8)]

6.1 Clinical Trials Experience

Because clinical trials are conducted under widely varying conditions, adverse reaction rates observed in the clinical trials of a drug cannot be directly compared to rates in the clinical trials of another drug and may not reflect the rates observed in practice.

Myelofibrosis

The safety of Jakafi was assessed in 617 patients in six clinical studies with a median duration of follow-up of 10.9 months, including 301 patients with MF in two Phase 3 studies.

In these two Phase 3 studies, patients had a median duration of exposure to Jakafi of 9.5 months (range 0.5 to 17 months), with 89% of patients treated for more than 6 months and 25% treated for more than 12 months. One hundred and eleven (111) patients started treatment at 15 mg twice daily and 190 patients started at 20 mg twice daily. In patients starting treatment with 15 mg twice daily (pretreatment platelet counts of 100 to 200 x 10^9/L) and 20 mg twice daily (pretreatment platelet counts greater than 200 x 10^9/L), 65% and 25% of patients, respectively, required a dose reduction below the starting dose within the first 8 weeks of therapy.

In a double-blind, randomized, placebo-controlled study of Jakafi, among the 155 patients treated with Jakafi, the most frequent adverse reactions were thrombocytopenia and anemia [see Table 13]. Thrombocytopenia, anemia and neutropenia are dose-related effects. The three most frequent nonhematologic adverse reactions were bruising, dizziness and headache [see Table 12].

Discontinuation for adverse events, regardless of causality, was observed in 11% of patients treated with Jakafi and 11% of patients treated with placebo.

Table 12 presents the most common nonhematologic adverse reactions occurring in patients who received Jakafi in the double-blind, placebo-controlled study during randomized treatment.

Table 12: Myelofibrosis: Nonhematologic Adverse Reactions Occurring in Patients on Jakafi in the Double-blind, Placebo-controlled Study During Randomized Treatment
 | Jakafi (N=155) |  |  | Placebo (N=151)
Adverse Reactions | All Grades [National Cancer Institute Common Terminology Criteria for Adverse Events (CTCAE), version 3.0] (%) | Grade 3 (%) | Grade 4 (%) | All Grades (%) | Grade 3 (%) | Grade 4 (%)
Bruising [includes contusion, ecchymosis, hematoma, injection site hematoma, periorbital hematoma, vessel puncture site hematoma, increased tendency to bruise, petechiae, purpura] | 23 | < 1 | 0 | 15 | 0 | 0
Dizziness [includes dizziness, postural dizziness, vertigo, balance disorder, Meniere’s Disease, labyrinthitis] | 18 | < 1 | 0 | 7 | 0 | 0
Headache | 15 | 0 | 0 | 5 | 0 | 0
Urinary Tract Infections [includes urinary tract infection, cystitis, urosepsis, urinary tract infection bacterial, kidney infection, pyuria, bacteria urine, bacteria urine identified, nitrite urine present] | 9 | 0 | 0 | 5 | < 1 | < 1
Weight Gain [includes weight increased, abnormal weight gain] | 7 | < 1 | 0 | 1 | < 1 | 0
Flatulence | 5 | 0 | 0 | < 1 | 0 | 0
Herpes Zoster [includes herpes zoster and post-herpetic neuralgia] | 2 | 0 | 0 | < 1 | 0 | 0

Description of Selected Adverse Reactions

Anemia

In the two Phase 3 clinical studies, median time to onset of first CTCAE Grade 2 or higher anemia was approximately 6 weeks. One patient (< 1%) discontinued treatment because of anemia. In patients receiving Jakafi, mean decreases in hemoglobin reached a nadir of approximately 1.5 to 2.0 g/dL below baseline after 8 to 12 weeks of therapy and then gradually recovered to reach a new steady state that was approximately 1.0 g/dL below baseline. This pattern was observed in patients regardless of whether they had received transfusions during therapy.

In the randomized, placebo-controlled study, 60% of patients treated with Jakafi and 38% of patients receiving placebo received red blood cell transfusions during randomized treatment. Among transfused patients, the median number of units transfused per month was 1.2 in patients treated with Jakafi and 1.7 in placebo treated patients.

Thrombocytopenia

In the two Phase 3 clinical studies, in patients who developed Grade 3 or 4 thrombocytopenia, the median time to onset was approximately 8 weeks. Thrombocytopenia was generally reversible with dose reduction or dose interruption. The median time to recovery of platelet counts above 50 x 10^9/L was 14 days. Platelet transfusions were administered to 5% of patients receiving Jakafi and to 4% of patients receiving control regimens. Discontinuation of treatment because of thrombocytopenia occurred in < 1% of patients receiving Jakafi and < 1% of patients receiving control regimens. Patients with a platelet count of 100 x 10^9/L to 200 x 10^9/L before starting Jakafi had a higher frequency of Grade 3 or 4 thrombocytopenia compared to patients with a platelet count greater than 200 x 10^9/L (17% versus 7%).

Neutropenia

In the two Phase 3 clinical studies, 1% of patients reduced or stopped Jakafi because of neutropenia.

Table 13 provides the frequency and severity of clinical hematology abnormalities reported for patients receiving treatment with Jakafi or placebo in the placebo-controlled study.

Table 13: Myelofibrosis: Worst Hematology Laboratory Abnormalities in the Placebo-Controlled Study [Presented values are worst Grade values regardless of baseline]
 | Jakafi (N=155) |  |  | Placebo (N=151)
Laboratory Parameter | All Grades [National Cancer Institute Common Terminology Criteria for Adverse Events, version 3.0] (%) | Grade 3 (%) | Grade 4 (%) | All Grades (%) | Grade 3 (%) | Grade 4 (%)
Thrombocytopenia | 70 | 9 | 4 | 31 | 1 | 0
Anemia | 96 | 34 | 11 | 87 | 16 | 3
Neutropenia | 19 | 5 | 2 | 4 | < 1 | 1

Additional Data from the Placebo-Controlled Study

- 25% of patients treated with Jakafi and 7% of patients treated with placebo developed newly occurring or worsening Grade 1 abnormalities in alanine transaminase (ALT). The incidence of greater than or equal to Grade 2 elevations was 2% for Jakafi with 1% Grade 3 and no Grade 4 ALT elevations.

- 17% of patients treated with Jakafi and 6% of patients treated with placebo developed newly occurring or worsening Grade 1 abnormalities in aspartate transaminase (AST). The incidence of Grade 2 AST elevations was < 1% for Jakafi with no Grade 3 or 4 AST elevations.

- 17% of patients treated with Jakafi and < 1% of patients treated with placebo developed newly occurring or worsening Grade 1 elevations in cholesterol. The incidence of Grade 2 cholesterol elevations was < 1% for Jakafi with no Grade 3 or 4 cholesterol elevations.

Polycythemia Vera

In a randomized, open-label, active-controlled study, 110 patients with PV resistant to or intolerant of hydroxyurea received Jakafi and 111 patients received best available therapy [see Clinical Studies (14.2)]. The most frequent adverse reaction was anemia. Discontinuation for adverse events, regardless of causality, was observed in 4% of patients treated with Jakafi. Table 14 presents the most frequent nonhematologic adverse reactions occurring up to Week 32.

Table 14: Polycythemia Vera: Nonhematologic Adverse Reactions Occurring in ≥ 5% of Patients on Jakafi in the Open-Label, Active-controlled Study up to Week 32 of Randomized Treatment
 | Jakafi (N=110) |  | Best Available Therapy (N=111)
Adverse Reactions | All Grades [National Cancer Institute Common Terminology Criteria for Adverse Events (CTCAE), version 3.0] (%) | Grade 3-4 (%) | All Grades (%) | Grade 3-4 (%)
Diarrhea | 15 | 0 | 7 | < 1
Dizziness [includes dizziness and vertigo] | 15 | 0 | 13 | 0
Dyspnea [includes dyspnea and dyspnea exertional] | 13 | 3 | 4 | 0
Muscle Spasms | 12 | < 1 | 5 | 0
Constipation | 8 | 0 | 3 | 0
Herpes Zoster [includes herpes zoster and post-herpetic neuralgia] | 6 | < 1 | 0 | 0
Nausea | 6 | 0 | 4 | 0
Weight Gain [includes weight increased and abnormal weight gain] | 6 | 0 | < 1 | 0
Urinary Tract Infections [includes urinary tract infection and cystitis] | 6 | 0 | 3 | 0
Hypertension | 5 | < 1 | 3 | < 1

Clinically relevant laboratory abnormalities are shown in Table 15.

Table 15: Polycythemia Vera: Selected Laboratory Abnormalities in the Open-Label, Active-controlled Study up to Week 32 of Randomized Treatment [Presented values are worst Grade values regardless of baseline]
 | Jakafi (N=110) |  |  | Best Available Therapy (N=111)
Laboratory Parameter | All Grades [National Cancer Institute Common Terminology Criteria for Adverse Events, version 3.0] (%) | Grade 3 (%) | Grade 4 (%) | All Grades (%) | Grade 3 (%) | Grade 4 (%)
Hematology
Anemia | 72 | < 1 | < 1 | 58 | 0 | 0
Thrombocytopenia | 27 | 5 | < 1 | 24 | 3 | < 1
Neutropenia | 3 | 0 | < 1 | 10 | < 1 | 0
Chemistry
Hypercholesterolemia | 35 | 0 | 0 | 8 | 0 | 0
Elevated ALT | 25 | < 1 | 0 | 16 | 0 | 0
Elevated AST | 23 | 0 | 0 | 23 | < 1 | 0
Hypertriglyceridemia | 15 | 0 | 0 | 13 | 0 | 0

Acute Graft-Versus-Host Disease

In a single-arm, open-label study, 71 adults (ages 18-73 years) were treated with Jakafi for aGVHD failing treatment with steroids with or without other immunosuppressive drugs [see Clinical Studies (14.3)]. The median duration of treatment with Jakafi was 46 days (range, 4‑382 days).

There were no fatal adverse reactions to Jakafi. An adverse reaction resulting in treatment discontinuation occurred in 31% of patients. The most common adverse reaction leading to treatment discontinuation was infection (10%). Table 16 shows the adverse reactions other than laboratory abnormalities.

Table 16: Acute Graft-Versus-Host Disease: Nonhematologic Adverse Reactions Occurring in ≥ 15% of Patients in the Open-Label, Single-Cohort Study
 | Jakafi (N=71)
Adverse Reactions [Selected laboratory abnormalities are listed in Table 17 below] | All Grades [National Cancer Institute Common Terminology Criteria for Adverse Events, version 4.03] (%) | Grade 3-4 (%)
Infections (pathogen not specified) | 55 | 41
Edema | 51 | 13
Hemorrhage | 49 | 20
Fatigue | 37 | 14
Bacterial infections | 32 | 28
Dyspnea | 32 | 7
Viral infections | 31 | 14
Thrombosis | 25 | 11
Diarrhea | 24 | 7
Rash | 23 | 3
Headache | 21 | 4
Hypertension | 20 | 13
Dizziness | 16 | 0

Selected laboratory abnormalities during treatment with Jakafi are shown in Table 17.

Table 17: Acute Graft-Versus-Host Disease: Selected Laboratory Abnormalities Worsening from Baseline in the Open-Label, Single Cohort Study
 | Jakafi (N=71)
 | Worst grade during treatment
Laboratory Parameter | All Grades [National Cancer Institute Common Terminology Criteria for Adverse Events, version 4.03] (%) | Grade 3-4 (%)
Hematology
Anemia | 75 | 45
Thrombocytopenia | 75 | 61
Neutropenia | 58 | 40
Chemistry
Elevated ALT | 48 | 8
Elevated AST | 48 | 6
Hypertriglyceridemia | 11 | 1

Chronic Graft-Versus-Host Disease

In a Phase 3, randomized, open-label, multi-center study, 165 patients were treated with Jakafi and 158 patients were treated with best available therapy for cGVHD failing treatment with steroids with or without other immunosuppressive drugs [see Clinical Studies (14.4)]; sixty-five patients crossed over from best available therapy to treatment with Jakafi, for a total of 230 patients treated with Jakafi. The median duration of exposure to Jakafi for the study was 49.7 weeks (range, 0.7 to 144.9 weeks) in the Jakafi arm. One hundred and nine (47%) patients were on Jakafi for at least 1 year.

There were five fatal adverse reactions to Jakafi, including 1 from toxic epidermal necrolysis and 4 from neutropenia, anemia and/or thrombocytopenia. An adverse reaction resulting in treatment discontinuation occurred in 18% of patients treated with Jakafi. An adverse reaction resulting in dose modification occurred in 27%, and an adverse reaction resulting in treatment interruption occurred in 23%. The most common hematologic adverse reactions (incidence > 35%) are anemia and thrombocytopenia. The most common nonhematologic adverse reactions (incidence ≥ 20%) are infections (pathogen not specified) and viral infection.

Table 18 presents the most frequent nonlaboratory adverse reactions occurring up to Cycle 7 Day 1 of randomized treatment.

Table 18: Chronic Graft-Versus-Host Disease: All-Grade (≥ 10%) and Grades 3-5 (≥ 3%) Nonlaboratory Adverse Reactions Occurring in Patients in the Open-Label, Active-controlled Study up to Cycle 7 Day 1 of Randomized Treatment
Adverse Reaction [Grouped terms that are composites of applicable adverse reaction terms.] | Jakafi (N = 165) |  | Best Available Therapy (N = 158)
Adverse Reaction [Grouped terms that are composites of applicable adverse reaction terms.] | All Grades [National Cancer Institute Common Terminology Criteria for Adverse Events (CTCAE), version 4.03] (%) | Grade ≥ 3 (%) | All Grades (%) | Grade ≥ 3 (%)
Infections and infestations
Infections (pathogen not specified) | 45 | 15 | 44 | 16
Viral infections | 28 | 5 | 23 | 5
Musculoskeletal and connective tissue disorders
Musculoskeletal pain | 18 | 1 | 13 | 0
General disorders and administration site conditions
Pyrexia | 16 | 2 | 9 | 1
Fatigue | 13 | 1 | 10 | 2
Edema | 10 | 1 | 12 | 1
Vascular disorders
Hypertension | 16 | 5 | 13 | 7
Hemorrhage | 12 | 2 | 15 | 2
Respiratory, thoracic and mediastinal disorders
Cough | 13 | 0 | 8 | 0
Dyspnea | 11 | 1 | 8 | 1
Gastrointestinal disorders
Nausea | 12 | 0 | 13 | 2
Diarrhea | 10 | 1 | 13 | 1

Clinically relevant laboratory abnormalities are shown in Table 19.

Table 19: Chronic Graft-Versus-Host Disease: Selected Laboratory Abnormalities in the Open-Label, Active-controlled Study up to Cycle 7 Day 1 of Randomized Treatment [Presented values are worst Grade values regardless of baseline]
Laboratory Test | Jakafi (N = 165) |  | Best Available Therapy (N = 158)
Laboratory Test | All Grades [National Cancer Institute Common Terminology Criteria for Adverse Events, version 4.03] (%) | Grade ≥ 3 (%) | All Grades (%) | Grade ≥ 3 (%)
Hematology
Anemia | 82 | 13 | 75 | 8
Neutropenia | 27 | 12 | 23 | 9
Thrombocytopenia | 58 | 20 | 54 | 17
Chemistry
Hypercholesterolemia | 88 | 10 | 85 | 8
Elevated AST | 65 | 5 | 54 | 6
Elevated ALT | 73 | 11 | 71 | 16
Gamma glutamyltransferase increased | 81 | 42 | 75 | 38
Creatinine increased | 47 | 1 | 40 | 2
Elevated lipase | 38 | 12 | 30 | 9
Elevated amylase | 35 | 8 | 25 | 4

6.2 Postmarketing Experience

The following adverse reactions have been identified during post-approval use of Jakafi. Because these reactions are reported voluntarily from a population of uncertain size, it is not always possible to reliably estimate their frequency or establish a causal relationship to drug exposure:

- Infections and Infestations: Herpes simplex virus reactivation and/or dissemination

7. DRUG INTERACTIONS

7.1 Effect of Other Drugs on Jakafi

Fluconazole

Concomitant use of Jakafi with fluconazole increases ruxolitinib exposure [see Clinical Pharmacology (12.3)], which may increase the risk of exposure-related adverse reactions. Avoid concomitant use of Jakafi with fluconazole doses of greater than 200 mg daily. Reduce the Jakafi dosage when used concomitantly with fluconazole doses of less than or equal to 200 mg [see Dosage and Administration (2.6)].

Strong CYP3A4 Inhibitors

Concomitant use of Jakafi with strong CYP3A4 inhibitors increases ruxolitinib exposure [see Clinical Pharmacology (12.3)], which may increase the risk of exposure-related adverse reactions. Reduce the Jakafi dosage when used concomitantly with strong CYP3A4 inhibitors except in patients with aGVHD or cGVHD [see Dosage and Administration (2.6)].

Strong CYP3A4 Inducers

Concomitant use of Jakafi with strong CYP3A4 inducers may decrease ruxolitinib exposure [see Clinical Pharmacology (12.3)], which may reduce efficacy of Jakafi. Monitor patients frequently and adjust the Jakafi dose based on safety and efficacy [see Clinical Pharmacology (12.3)].

8. USE IN SPECIFIC POPULATIONS

8.1 Pregnancy

Risk Summary

When pregnant rats and rabbits were administered ruxolitinib during the period of organogenesis adverse developmental outcomes occurred at doses associated with maternal toxicity (see Data). There are no studies with the use of Jakafi in pregnant women to inform drug-associated risks.

The background risk of major birth defects and miscarriage for the indicated populations is unknown. Adverse outcomes in pregnancy occur regardless of the health of the mother or the use of medications. The background risk in the U.S. general population of major birth defects is 2% to 4% and miscarriage is 15% to 20% of clinically recognized pregnancies.

Data

Animal Data

Ruxolitinib was administered orally to pregnant rats or rabbits during the period of organogenesis, at doses of 15, 30 or 60 mg/kg/day in rats and 10, 30 or 60 mg/kg/day in rabbits. There were no treatment-related malformations. Adverse developmental outcomes, such as decreases of approximately 9% in fetal weights were noted in rats at the highest and maternally toxic dose of 60 mg/kg/day. This dose results in an exposure (AUC) that is approximately 2 times the clinical exposure at the maximum recommended dose of 25 mg twice daily. In rabbits, lower fetal weights of approximately 8% and increased late resorptions were noted at the highest and maternally toxic dose of 60 mg/kg/day. This dose is approximately 7% the clinical exposure at the maximum recommended dose.

In a pre- and post-natal development study in rats, pregnant animals were dosed with ruxolitinib from implantation through lactation at doses up to 30 mg/kg/day. There were no drug-related adverse findings in pups for fertility indices or for maternal or embryofetal survival, growth and development parameters at the highest dose evaluated (34% the clinical exposure at the maximum recommended dose of 25 mg twice daily).

8.2 Lactation

Risk Summary

No data are available regarding the presence of ruxolitinib in human milk, the effects on the breast fed child, or the effects on milk production. Ruxolitinib and/or its metabolites were present in the milk of lactating rats (see Data). Because many drugs are present in human milk and because of the potential for thrombocytopenia and anemia shown for Jakafi in human studies, discontinue breastfeeding during treatment with Jakafi and for two weeks after the final dose.

Data

Animal Data

Lactating rats were administered a single dose of [^14C]-labeled ruxolitinib (30 mg/kg) on postnatal Day 10, after which plasma and milk samples were collected for up to 24 hours. The AUC for total radioactivity in milk was approximately 13-fold the maternal plasma AUC. Additional analysis showed the presence of ruxolitinib and several of its metabolites in milk, all at levels higher than those in maternal plasma.

8.4 Pediatric Use

Myelofibrosis

The safety and effectiveness of Jakafi for treatment of myelofibrosis in pediatric patients have not been established.

Polycythemia Vera

The safety and effectiveness of Jakafi for treatment of polycythemia vera in pediatric patients have not been established.

Acute Graft-Versus-Host Disease

The safety and effectiveness of Jakafi for treatment of steroid-refractory aGVHD has been established for treatment of pediatric patients 12 years and older. Use of Jakafi in pediatric patients with steroid-refractory aGVHD is supported by evidence from adequate and well-controlled trials of Jakafi in adults [see Clinical Studies (14.3)] and additional pharmacokinetic and safety data in pediatric patients. The safety and effectiveness of Jakafi for treatment of steroid-refractory aGVHD has not been established in pediatric patients younger than 12 years old.

Chronic Graft-Versus-Host Disease

The safety and effectiveness of Jakafi for treatment of cGVHD after failure of one or two lines of systemic therapy has been established for treatment of pediatric patients 12 years and older. Use of Jakafi in pediatric patients with cGVHD after failure of one or two lines of systemic therapy is supported by evidence from adequate and well-controlled trials of Jakafi in adults and adolescents [see Clinical Studies (14.4)] and additional pharmacokinetic and safety data in pediatric patients. The safety and effectiveness of Jakafi for treatment of cGVHD has not been established in pediatric patients younger than 12 years old.

Other Myeloproliferative Neoplasms, Leukemias, and Solid Tumors

The safety and effectiveness of ruxolitinib were assessed but not established in a single-arm trial (NCT01164163) in patients with relapsed or refractory solid tumors, leukemias, or myeloproliferative neoplasms. The patients included 18 children (age 2 to < 12 years) and 14 adolescents (age 12 to < 17 years). Overall, 19% of patients received more than one cycle. No new safety signals were observed in pediatric patients in this trial.

The safety and effectiveness of ruxolitinib in combination with chemotherapy for treatment of high-risk, de novo CRLF2 rearranged or JAK pathway–mutant Ph-like acute lymphoblastic leukemia (ALL) were assessed but not established in a single-arm trial (NCT02723994). The patients included 2 infants (age < 2 years), 42 children (age 2 to < 12 years) and 62 adolescents (age 12 to < 17 years). No new safety signals were observed in pediatric patients in this trial.

Juvenile Animal Toxicity Data

Administration of ruxolitinib to juvenile rats resulted in effects on growth and bone measures. When administered starting at postnatal day 7 (the equivalent of a human newborn) at doses of 1.5 to 75 mg/kg/day, evidence of fractures occurred at doses ≥ 30 mg/kg/day, and effects on body weight and other bone measures [e.g., bone mineral content, peripheral quantitative computed tomography, and x-ray analysis] occurred at doses ≥ 5 mg/kg/day. When administered starting at postnatal day 21 (the equivalent of a human 2-3 years of age) at doses of 5 to 60 mg/kg/day, effects on body weight and bone occurred at doses ≥ 15 mg/kg/day, which were considered adverse at 60 mg/kg/day. Males were more severely affected than females in all age groups, and effects were generally more severe when administration was initiated earlier in the postnatal period. These findings were observed at exposures that are at least 27% the clinical exposure at the maximum recommended dose of 25 mg twice daily.

8.5 Geriatric Use

Of the total number of patients with MF in clinical studies with Jakafi, 52% were 65 years and older, while 15% were 75 years and older. No overall differences in safety or effectiveness of Jakafi were observed between these patients and younger patients.

Clinical studies of Jakafi in patients with aGVHD did not include sufficient numbers of subjects age 65 and over to determine whether they respond differently from younger subjects.

Of the total number of patients with cGVHD treated with Jakafi in clinical trials, 11% were 65 years and older. No overall differences in safety or effectiveness of Jakafi were observed between these patients and younger patients.

8.6 Renal Impairment

Total exposure of ruxolitinib and its active metabolites increased with moderate (CLcr 30 to 59 mL/min) and severe (CLcr 15 to 29 mL/min) renal impairment, and ESRD (CLcr less than 15 mL/min) on dialysis [see Clinical Pharmacology (12.3)]. Modify Jakafi dosage as recommended [see Dosage and Administration (2.7)].

8.7 Hepatic Impairment

Exposure of ruxolitinib increased with mild (Child-Pugh A), moderate (Child-Pugh B) and severe (Child-Pugh C) hepatic impairment [see Clinical Pharmacology (12.3)].

Reduce Jakafi dosage as recommended in patients with MF or PV with hepatic impairment [see Dosage and Administration (2.7)]. Reduce Jakafi dosage as recommended for patients with Stage 4 liver aGVHD.

Monitor blood counts more frequently for toxicity and modify the Jakafi dosage for adverse reactions if they occur for patients with Score 3 liver cGVHD [see Dosage and Administration (2.7) and Clinical Pharmacology (12.3)].

10. OVERDOSAGE

There is no known antidote for overdoses with Jakafi. Single doses up to 200 mg have been given with acceptable acute tolerability. Higher than recommended repeat doses are associated with increased myelosuppression including leukopenia, anemia and thrombocytopenia. Appropriate supportive treatment should be given.

Hemodialysis is not expected to enhance the elimination of Jakafi.

11. DESCRIPTION

Ruxolitinib phosphate is a kinase inhibitor with the chemical name (R)-3-(4-(7H-pyrrolo[2,3-d]pyrimidin-4-yl)-1H-pyrazol-1-yl)-3-cyclopentylpropanenitrile phosphate and a molecular weight of 404.36. Ruxolitinib phosphate has the following structural formula:

Ruxolitinib phosphate is a white to off-white to light pink powder and is soluble in aqueous buffers across a pH range of 1 to 8.

Jakafi (ruxolitinib) Tablets are for oral administration. Each tablet contains 6.6 mg, 13.2 mg, 19.8 mg, 26.4 mg, or 33 mg of ruxolitinib phosphate equivalent to 5 mg, 10 mg, 15 mg, 20 mg, or 25 mg of ruxolitinib free base, respectively, together with microcrystalline cellulose, lactose monohydrate, magnesium stearate, colloidal silicon dioxide, sodium starch glycolate, povidone and hydroxypropyl cellulose.

12. CLINICAL PHARMACOLOGY

12.1 Mechanism of Action

Ruxolitinib, a kinase inhibitor, inhibits Janus Associated Kinases (JAKs) JAK1 and JAK2 which mediate the signaling of a number of cytokines and growth factors that are important for hematopoiesis and immune function. JAK signaling involves recruitment of STATs (signal transducers and activators of transcription) to cytokine receptors, activation and subsequent localization of STATs to the nucleus leading to modulation of gene expression.

MF and PV are myeloproliferative neoplasms (MPN) known to be associated with dysregulated JAK1 and JAK2 signaling. In a mouse model of JAK2V617F-positive MPN, oral administration of ruxolitinib prevented splenomegaly, preferentially decreased JAK2V617F mutant cells in the spleen and decreased circulating inflammatory cytokines (e.g., TNF-α, IL-6).

JAK-STAT signaling pathways play a role in regulating the development, proliferation, and activation of several immune cell types important for GVHD pathogenesis. In a mouse model of aGVHD, oral administration of ruxolitinib was associated with decreased expression of inflammatory cytokines in colon homogenates and reduced immune-cell infiltration in the colon.

12.2 Pharmacodynamics

Jakafi inhibits cytokine induced STAT3 phosphorylation in whole blood from patients with MF and PV. STAT3 phosphorylation reached maximal inhibition 2 hours after Jakafi dosing and returned to near baseline by 10 hours in patients with MF and PV.

Cardiac Electrophysiology

At a dose of 1.25 to 10 times the highest recommended starting dosage, Jakafi does not prolong the QT interval to any clinically relevant extent.

12.3 Pharmacokinetics

Mean ruxolitinib maximal plasma concentration (Cmax) and AUC increased proportionally over a single dose range of 5 mg to 200 mg (4 times the approved highest recommended total daily dosage of 25 mg twice daily). Mean ruxolitinib Cmax ranged from 205 nM to 7100 nM and AUC ranged from 862 nM*hr to 30700 nM*hr over a single dose range of 5 mg to 200 mg.

Absorption

Ruxolitinib achieves Cmax within 1 hour to 2 hours post-dose. Oral absorption of ruxolitinib is estimated to be at least 95%.

Effect of Food

No clinically relevant changes in the pharmacokinetics of ruxolitinib were observed upon administration of Jakafi with a high-fat, high-calorie meal (approximately 800 to 1000 calories of which 50% were derived from fat).

Distribution

The mean ruxolitinib volume of distribution at steady-state is 72 L (coefficient of variation [CV] 29%) in patients with MF and 75 L (23%) in patients with PV.

Protein binding of ruxolitinib is approximately 97%, mostly to albumin.

Elimination

The mean elimination half-life of ruxolitinib is approximately 3 hours and the mean elimination half-life of ruxolitinib and its metabolites is approximately 5.8 hours in healthy volunteers.

Ruxolitinib clearance (%CV) was 17.7 L/h in women and 22.1 L/h in men with MF (39%).

Ruxolitinib clearance (%CV) was 12.7 L/h (42%) in patients with PV.

Ruxolitinib clearance (%CV) was 11.8 L/h (63%) in patients with aGVHD.

Ruxolitinib clearance (%CV) was 9.7 L/h (51%) in patients with cGVHD.

Metabolism

Ruxolitinib is metabolized by CYP3A4 and to a lesser extent by CYP2C9.

Excretion

Following a single oral dose of radiolabeled ruxolitinib, 74% of radioactivity was excreted in urine and 22% via feces. Unchanged drug accounted for less than 1% of the excreted total radioactivity.

Specific Populations

No clinically relevant differences in ruxolitinib pharmacokinetics were observed based on age (12-73 years), race (White, Asian), sex, or weight (29-139 kg).

Patients with Renal Impairment

Total AUC of ruxolitinib and its active metabolites increased by 1.3-, 1.5-, 1.9-, and 1.6-fold in subjects with mild, moderate, severe renal impairment, and with ESRD after dialysis, respectively, compared to subjects with normal renal function (CLcr ≥ 90 mL/min). The change in the pharmacodynamic marker, pSTAT3 inhibition, was consistent with the corresponding increase in metabolite exposure with renal impairment. Ruxolitinib is not removed by dialysis; however, the removal of some active metabolites by dialysis cannot be ruled out.

Patients with Hepatic Impairment

No clinically relevant effect on ruxolitinib pharmacokinetics was observed based on mild to severe hepatic impairment by NCI criteria (total bilirubin > ULN and any AST) in patients with aGVHD or cGVHD.

Ruxolitinib AUC increased in subjects with mild (Child-Pugh A) by 1.9-fold, moderate (Child-Pugh B) by 1.3-fold, and severe (Child-Pugh C) hepatic impairment by 1.7-fold compared to that in subjects with normal hepatic function.

The change in the pharmacodynamic marker, pSTAT3 inhibition, was consistent with the corresponding increase in ruxolitinib exposure except in the severe hepatic impairment cohort where the pharmacodynamic activity was more prolonged in some subjects than expected based on plasma concentrations of ruxolitinib.

Patients with Liver Involvement in Graft-Versus-Host Disease

No clinically relevant effect on ruxolitinib pharmacokinetics was observed based on Stage 1, 2 or 3 liver aGVHD, or Score 1, or 2 liver cGVHD.

A lower apparent clearance of ruxolitinib was observed in patients with Stage 4 liver aGVHD compared to patients with no liver aGVHD.

The effect of Score 3 liver cGVHD on the pharmacokinetics of ruxolitinib is unknown.

Drug Interaction Studies

Clinical Studies and Model-Informed Approaches

Fluconazole: Fluconazole 100 to 400 mg once daily (a moderate CYP3A4 and CYP2C9 inhibitor) increases steady state ruxolitinib AUC by approximately 100% to 300% [see Dosage and Administration (2.6) and Drug Interactions (7)].

Strong CYP3A4 inhibitors: Ketoconazole (strong CYP3A4 inhibitor) increased ruxolitinib Cmax by 33% and AUC by 91% and prolonged ruxolitinib half-life from 3.7 hours to 6 hours [see Dosage and Administration (2.6) and Drug Interactions (7)].

Moderate CYP3A4 inhibitors: Erythromycin (moderate CYP3A4 inhibitor) increased ruxolitinib Cmax by 8% and AUC by 27% [see Drug Interactions (7)].

Strong CYP3A4 inducers: Rifampin (strong CYP3A4 inducer) decreased ruxolitinib Cmax by 32% and AUC by 61%. The relative exposure to ruxolitinib’s active metabolites increased approximately 100% [see Drug Interactions (7)].

In Vitro Studies

Cytochrome P450 (CYP) Enzymes: Ruxolitinib and its M18 metabolite did not inhibit CYP1A2, CYP2B6, CYP2C8, CYP2C9, CYP2C19, CYP2D6 or CYP3A4. Ruxolitinib did not induce CYP1A2, CYP2B6 or CYP3A4 at clinically relevant concentrations.

Transporter Systems: Ruxolitinib and its M18 metabolite did not inhibit the P-gp, BCRP, OATP1B1, OATP1B3, OCT1, OCT2, OAT1 or OAT3 at clinically relevant concentrations. Ruxolitinib was not a P-gp substrate.

13. NONCLINICAL TOXICOLOGY

13.1 Carcinogenesis, Mutagenesis, Impairment of Fertility

Ruxolitinib was not carcinogenic in the 6-month Tg.rasH2 transgenic mouse model or in a 2-year carcinogenicity study in the rat.

Ruxolitinib was not mutagenic in a bacterial mutagenicity assay (Ames test) or clastogenic in in vitro chromosomal aberration assay (cultured human peripheral blood lymphocytes) or in vivo in a rat bone marrow micronucleus assay.

In a fertility study, ruxolitinib was administered to male rats prior to and throughout mating and to female rats prior to mating and up to the implantation day (gestation day 7). Ruxolitinib had no effect on fertility or reproductive function in male or female rats at doses of 10, 30 or 60 mg/kg/day. However, in female rats doses of greater than or equal to 30 mg/kg/day resulted in increased post-implantation loss. The exposure (AUC) at the dose of 30 mg/kg/day is approximately 34% the clinical exposure at the maximum recommended dose of 25 mg twice daily.

14. CLINICAL STUDIES

14.1 Myelofibrosis

Two randomized Phase 3 studies (Studies 1 and 2) were conducted in patients with MF (either primary MF, post-polycythemia vera MF or post-essential thrombocythemia-MF). In both studies, patients had palpable splenomegaly at least 5 cm below the costal margin and risk category of intermediate 2 (2 prognostic factors) or high risk (3 or more prognostic factors) based on the International Working Group Consensus Criteria (IWG).

The starting dose of Jakafi was based on platelet count. Patients with a platelet count between 100 and 200 x 10^9/L were started on Jakafi 15 mg twice daily and patients with a platelet count greater than 200 x 10^9/L were started on Jakafi 20 mg twice daily. Doses were then individualized based upon tolerability and efficacy with maximum doses of 20 mg twice daily for patients with platelet counts between 100 to less than or equal to 125 x 10^9/L, of 10 mg twice daily for patients with platelet counts between 75 to less than or equal to 100 x 10^9/L, and of 5 mg twice daily for patients with platelet counts between 50 to less than or equal to 75 x 10^9/L.

Study 1

Study 1 (NCT00952289) was a double-blind, randomized, placebo-controlled study in 309 patients who were refractory to or were not candidates for available therapy. The median age was 68 years (range 40 to 91 years) with 61% of patients older than 65 years and 54% were male. Fifty percent (50%) of patients had primary MF, 31% had post-polycythemia vera MF and 18% had post-essential thrombocythemia MF. Twenty-one percent (21%) of patients had red blood cell transfusions within 8 weeks of enrollment in the study. The median hemoglobin count was 10.5 g/dL and the median platelet count was 251 x 10^9/L. Patients had a median palpable spleen length of 16 cm below the costal margin, with 81% having a spleen length 10 cm or greater below the costal margin. Patients had a median spleen volume as measured by magnetic resonance imaging (MRI) or computed tomography (CT) of 2595 cm^3 (range 478 cm^3 to 8881 cm^3). (The upper limit of normal is approximately 300 cm^3).

Patients were dosed with Jakafi or matching placebo. The primary efficacy endpoint was the proportion of patients achieving greater than or equal to a 35% reduction from baseline in spleen volume at Week 24 as measured by MRI or CT.

Secondary endpoints included duration of a 35% or greater reduction in spleen volume and proportion of patients with a 50% or greater reduction in Total Symptom Score from baseline to Week 24 as measured by the modified Myelofibrosis Symptom Assessment Form (MFSAF) v2.0 diary.

Study 2

Study 2 (NCT00934544) was an open-label, randomized study in 219 patients. Patients were randomized 2:1 to Jakafi versus best available therapy. Best available therapy was selected by the investigator on a patient-by-patient basis. In the best available therapy arm, the medications received by more than 10% of patients were hydroxyurea (47%) and glucocorticoids (16%). The median age was 66 years (range 35 to 85 years) with 52% of patients older than 65 years and 57% were male. Fifty-three percent (53%) of patients had primary MF, 31% had post-polycythemia vera MF and 16% had post-essential thrombocythemia MF. Twenty-one percent (21%) of patients had red blood cell transfusions within 8 weeks of enrollment in the study. The median hemoglobin count was 10.4 g/dL and the median platelet count was 236 x 10^9/L. Patients had a median palpable spleen length of 15 cm below the costal margin, with 70% having a spleen length 10 cm or greater below the costal margin. Patients had a median spleen volume as measured by MRI or CT of 2381 cm^3 (range 451 cm^3 to 7765 cm^3).

The primary efficacy endpoint was the proportion of patients achieving 35% or greater reduction from baseline in spleen volume at Week 48 as measured by MRI or CT.

A secondary endpoint in Study 2 was the proportion of patients achieving a 35% or greater reduction of spleen volume as measured by MRI or CT from baseline to Week 24.

Study 1 and 2 Efficacy Results

Efficacy analyses of the primary endpoint in Studies 1 and 2 are presented in Table 20 below. A significantly larger proportion of patients in the Jakafi group achieved a 35% or greater reduction in spleen volume from baseline in both studies compared to placebo in Study 1 and best available therapy in Study 2. A similar proportion of patients in the Jakafi group achieved a 50% or greater reduction in palpable spleen length.

Table 20: Percent of Patients with Myelofibrosis Achieving 35% or Greater Reduction from Baseline in Spleen Volume at Week 24 in Study 1 and at Week 48 in Study 2 (Intent to Treat)
 | Study 1 |  | Study 2
 | Jakafi (N=155) | Placebo (N=154) | Jakafi (N=146) | Best Available Therapy (N=73)
Time Points | Week 24 |  | Week 48
Number (%) of Patients with Spleen Volume Reduction by 35% or More | 65 (42) | 1 (< 1) | 41 (29) | 0
P-value | < 0.0001 |  | < 0.0001

Figure 1 shows the percent change from baseline in spleen volume for each patient at Week 24 (Jakafi N=139, placebo N=106) or the last evaluation prior to Week 24 for patients who did not complete 24 weeks of randomized treatment (Jakafi N=16, placebo N=47). One (1) patient (placebo) with a missing baseline spleen volume is not included.

In Study 1, MF symptoms were a secondary endpoint and were measured using the modified Myelofibrosis Symptom Assessment Form (MFSAF) v2.0 diary. The modified MFSAF is a daily diary capturing the core symptoms of MF (abdominal discomfort, pain under left ribs, night sweats, itching, bone/muscle pain and early satiety). Symptom scores ranged from 0 to 10 with 0 representing symptoms "absent" and 10 representing "worst imaginable" symptoms. These scores were added to create the daily total score, which has a maximum of 60.

Table 21 presents assessments of Total Symptom Score from baseline to Week 24 in Study 1 including the proportion of patients with at least a 50% reduction (ie, improvement in symptoms). At baseline, the mean Total Symptom Score was 18.0 in the Jakafi group and 16.5 in the placebo group. A higher proportion of patients in the Jakafi group had a 50% or greater reduction in Total Symptom Score than in the placebo group, with a median time to response of less than 4 weeks.

Table 21: Improvement in Total Symptom Score in Patients with Myelofibrosis
 | Jakafi (N=148) | Placebo (N=152)
Number (%) of Patients with 50% or Greater Reduction in Total Symptom Score by Week 24 | 68 (46) | 8 (5)
P-value | < 0.0001

Figure 2 shows the percent change from baseline in Total Symptom Score for each patient at Week 24 (Jakafi N=129, placebo N=103) or the last evaluation on randomized therapy prior to Week 24 for patients who did not complete 24 weeks of randomized treatment (Jakafi N=16, placebo N=42). Results are excluded for 5 patients with a baseline Total Symptom Score of zero, 8 patients with missing baseline and 6 patients with insufficient post-baseline data.

Figure 3 displays the proportion of patients with at least a 50% improvement in each of the individual symptoms that comprise the Total Symptom Score indicating that all 6 of the symptoms contributed to the higher Total Symptom Score response rate in the group treated with Jakafi.

An exploratory analysis of patients receiving Jakafi also showed improvement in fatigue-related symptoms (i.e., tiredness, exhaustion, mental tiredness, and lack of energy) and associated impacts on daily activities (i.e., activity limitations related to work, self-care, and exercise) as measured by the PROMIS® Fatigue 7-item short form total score at Week 24. Patients who achieved a reduction of 4.5 points or more from baseline to Week 24 in the PROMIS® Fatigue total score were considered to have achieved a fatigue response. Fatigue response was reported in 35% of patients in the Jakafi group versus 14% of the patients in the placebo group.

Overall survival was a secondary endpoint in both Study 1 and Study 2. Patients in the control groups were eligible for crossover in both studies, and the median times to crossover were 9 months in Study 1 and 17 months in Study 2.

Figure 4 and Figure 5 show Kaplan-Meier curves of overall survival at prospectively planned analyses after all patients remaining on study had completed 144 weeks on study.

14.2 Polycythemia Vera

Study 3 (NCT01243944) was a randomized, open-label, active-controlled Phase 3 study conducted in 222 patients with PV. Patients had been diagnosed with PV for at least 24 weeks, had an inadequate response to or were intolerant of hydroxyurea, required phlebotomy and exhibited splenomegaly. All patients were required to demonstrate hematocrit control between 40-45% prior to randomization. The age ranged from 33 to 90 years with 30% of patients over 65 years of age and 66% were male. Patients had a median spleen volume as measured by MRI or CT of 1272 cm^3 (range 254 cm^3 to 5147 cm^3) and median palpable spleen length below the costal margin was 7 cm.

Patients were randomized to Jakafi or best available therapy. The starting dose of Jakafi was 10 mg twice daily. Doses were then individualized based upon tolerability and efficacy with a maximum dose of 25 mg twice daily. At Week 32, 98 patients were still on Jakafi with 8% receiving greater than 20 mg twice daily, 15% receiving 20 mg twice daily, 33% receiving 15 mg twice daily, 34% receiving 10 mg twice daily, and 10% receiving less than 10 mg twice daily. Best available therapy (BAT) was selected by the investigator on a patient-by-patient basis and included hydroxyurea (60%), interferon/pegylated interferon (12%), anagrelide (7%), pipobroman (2%), lenalidomide/thalidomide (5%), and observation (15%).

The primary endpoint was the proportion of subjects achieving a response at Week 32, with response defined as having achieved both hematocrit control (the absence of phlebotomy eligibility beginning at the Week 8 visit and continuing through Week 32) and spleen volume reduction (a greater than or equal to 35% reduction from baseline in spleen volume at Week 32). Phlebotomy eligibility was defined as a confirmed hematocrit greater than 45% that is at least 3 percentage points higher than the hematocrit obtained at baseline or a confirmed hematocrit greater than 48%, whichever was lower. Secondary endpoints included the proportion of all randomized subjects who achieved the primary endpoint and who maintained their response 48 weeks after randomization, and the proportion of subjects achieving complete hematological remission at Week 32 with complete hematological remission defined as achieving hematocrit control, platelet count less than or equal to 400 x 10^9/L, and white blood cell count less than or equal to 10 x 10^9/L.

Results of the primary and secondary endpoints are presented in Table 22. A significantly larger proportion of patients on the Jakafi arm achieved a response for the primary endpoint compared to best available therapy at Week 32 and maintained their response 48 weeks after randomization. A significantly larger proportion of patients on the Jakafi arm compared to best available therapy also achieved complete hematological remission at Week 32.

Table 22: Percent of Patients with Polycythemia Vera Achieving the Primary and Key Secondary Endpoints in Study 3 (Intent to Treat)
 | Jakafi (N=110) | Best Available Therapy (N=112)
Number (%) of Patients Achieving a Primary Response at Week 32 | 25 (23%) | 1 (< 1%)
95% CI of the response rate (%) | (15%, 32%) | (0%, 5%)
P-value | < 0.0001
Number (%) of Patients Achieving a Durable Primary Response at Week 48 | 22 (20%) | 1 (< 1%)
95% CI of the response rate (%) | (13%, 29%) | (0%, 5%)
P-value | < 0.0001
Number (%) of Patients Achieving Complete Hematological Remission at Week 32 | 26 (24%) | 9 (8%)
95% CI of the response rate (%) | (16%, 33%) | (4%, 15%)
P-value | 0.0016
Primary Response defined as having achieved both the absence of phlebotomy eligibility beginning at the Week 8 visit and continuing through Week 32 and a greater than or equal to 35% reduction from baseline in spleen volume at Week 32.

Additional analyses for Study 3 to assess durability of response were conducted at Week 80 only in the Jakafi arm. On this arm, 91 (83%) patients were still on treatment at the time of the Week 80 data cut-off. Of the 25 patients who achieved a primary response at Week 32, 19 (76% of the responders) maintained their response through Week 80, and of the 26 patients who achieved complete hematological remission at Week 32, 15 (58% of the responders) maintained their response through Week 80.

In an assessment of the individual components that make up the primary endpoint, there were 66 (60%) patients with hematocrit control on the Jakafi arm vs. 21 (19%) patients on best available therapy at Week 32; 51 (77% of hematocrit responders) patients on the Jakafi arm maintained hematocrit control through Week 80. There were 44 (40%) patients with spleen volume reduction from baseline greater than or equal to 35% on the Jakafi arm vs. 1 (< 1%) patient on best available therapy at Week 32; 43 (98% of spleen volume reduction responders) patients on the Jakafi arm maintained spleen volume reduction through Week 80.

14.3 Acute Graft-Versus-Host Disease

Study 4 (NCT02953678) was an open-label, single-arm, multicenter study of Jakafi for treatment of patients with steroid-refractory aGVHD Grades 2 to 4 (Mount Sinai Acute GVHD International Consortium (MAGIC) criteria) occurring after allogeneic hematopoietic stem cell transplantation. Jakafi was administered at 5 mg twice daily, and the dose could be increased to 10 mg twice daily after 3 days in the absence of toxicity.

There were 49 patients with aGVHD refractory to steroids alone. These patients had a median age of 57 years (range, 18-72 years), 47% were male, 92% were Caucasian, and 14% were Hispanic. At baseline, aGVHD was Grade 2 in 27%, Grade 3 in 55%, and Grade 4 in 18%; 84% had visceral GVHD; the median MAGIC biomarker score was 0.47 (range, 0.10‑0.92); and the median ST2 level was 334 mcg/L (range, 55-1286 mcg/L). The median duration of prior corticosteroid exposure at baseline was 15 days (range: 3 - 106 days).

The efficacy of Jakafi was based on Day-28 overall response rate (ORR) (complete response, very good partial response or partial response by Center for International Blood and Marrow Transplant Research (CIBMTR) criteria) and the duration of response. The ORR results are presented in Table 23; Day-28 ORR was 100% for Grade 2 GVHD, 40.7% for Grade 3 GVHD, and 44.4% for Grade 4 GVHD.

The median duration of response, calculated from Day-28 response to progression, new salvage therapy for aGVHD or death from any cause (with progression being defined as worsening by one stage in any organ without improvement in other organs in comparison to prior response assessment) was 16 days (95% CI 9, 83). Also, for the Day-28 responders, the median time from Day-28 response to either death or need for new therapy for aGVHD (additional salvage therapy or increase in steroids) was 173 days (95% CI 66, NE).

Table 23: Day-28 Overall Response Rate for Patients with Steroid-Refractory Acute GVHD in Study 4
 | Refractory to Steroids Alone (n=49)
Overall Response (%) (95% CI) | 28 (57.1%) (42.2, 71.2)
Complete Response | 15 (30.6%)
Very Good Partial Response | 2 (4.1%)
Partial Response | 11 (22.4%)

14.4 Chronic Graft-Versus-Host Disease

Study 5 (REACH-3; NCT03112603) was a randomized, open-label, multicenter study of Jakafi in comparison to best available therapy (BAT) for treatment of corticosteroid-refractory cGVHD after allogeneic stem cell transplantation. Eligible patients were ≥ 12 years old with moderate or severe cGVHD as defined by NIH Consensus Criteria requiring additional therapy after failure of corticosteroid therapy and no more than one additional salvage treatment. Patients were excluded if they had ANC < 1 Gi/L and platelet count < 25 Gi/L, estimated creatinine clearance < 30 ml/min, progressive onset cGVHD, oxygen saturation < 90%, total bilirubin > 2 mg/dL, or diarrhea due to GVHD.

A total of 329 patients were randomized 1:1 to receive either Jakafi 10 mg twice daily (n=165) or BAT (n=164). BAT was selected by the investigator prior to randomization and included the following treatments: extracorporeal photopheresis (ECP), low-dose methotrexate (MTX), mycophenolate mofetil (MMF), mTOR inhibitors (everolimus or sirolimus), infliximab, rituximab, pentostatin, imatinib, or ibrutinib. Randomization was stratified by cGVHD severity (moderate versus severe). On Cycle 7 Day 1 and thereafter, patients randomized to BAT could cross over to Jakafi if they had disease progression, mixed response, unchanged response, cGVHD flare, or toxicity to BAT. All patients also received standard supportive care, including anti-infective medications. GVHD prophylaxis and cGVHD treatment medications initiated before randomization, including systemic corticosteroids, calcineurin inhibitors, and topical or inhaled corticosteroid therapy, were allowed to be continued per institutional guidelines. Table 24 shows the demographics and baseline disease characteristics of the randomized population.

Table 24: REACH-3: Demographics and Baseline Chronic GVHD Characteristics
 | Jakafi (N=165) | Best Available Therapy (N=164)
Median Age, Years (range) | 49 (13, 73) | 50 (12, 76)
Age 12 to < 18 Year, n (%) | 4 (2) | 8 (5)
Age > 65 Years, n (%) | 18 (11) | 22 (13)
Male, n (%) | 109 (66) | 92 (56)
Race, n (%)
White | 116 (70) | 132 (81)
Black | 2 (1) | 0
Asian | 33 (20) | 21 (13)
American Indian or Alaska native | 2 (1) | 0
Other | 9 (6) | 4 (2)
Unknown | 3 (2) | 7 (4)
Median (range) time (days) from cGVHD diagnosis to randomization | 174 (7-2017) | 150 (10-1947)
Prior Therapy
No prior treatment for cGVHD | 2 (1) | 1 (1)
Failed first-line steroids alone | 115 (70) | 125 (76)
Failed first-line combination including steroids | 42 (25) | 30 (18)
Failed two lines of therapy | 6 (4) | 8 (5)
≥ 4 Organs involved, n (%) | 67 (41) | 63 (38)
Severe cGVHD, n (%) | 86 (52) | 79 (48)
Median (range) cGVHD Total Symptom Score | 19 (0-80) | 18 (1-54)
Median (range) corticosteroid dose at baseline (PE mg/kg) [Prednisone equivalent milligrams/kilogram] | 0.29 (0.01-1.81) | 0.26 (0.06-1.21)

The efficacy of Jakafi was based on overall response rate (ORR) through Cycle 7 Day 1, where overall response included complete response or partial response according to the 2014 NIH Response Criteria and durability of the response. The ORR results are presented in Table 25; the difference in ORR between Jakafi and BAT arms was 13% (95% CI 3%, 23%). The median time to first response in the responders was 3 weeks (range, 2 to 24) for the Jakafi arm and 4 weeks (range, 2 to 25) for the BAT arm. The median duration of response, calculated from first response to progression, death, or new systemic therapies for cGVHD, was 4.2 months (95% CI 3.2, 6.7) for the Jakafi arm and 2.1 months (95% CI 1.6, 3.2) for the BAT arm; and the median time from first response to death or new systemic therapies for cGVHD was 25 months (95% CI 16.8, NE) for the Jakafi arm and 5.6 months (95% CI 4.1, 7.8) for the BAT arm.

Table 25: Overall Response Rate through Cycle 7 Day 1 for Patients with Chronic GVHD in Study 5
 | Jakafi (N=165) | Best Available Therapy (N=164)
Overall Response (%) (95% CI) [95% CI of Overall Response Rate is estimated using Clopper-Pearson method.] | 116 (70%) (63%, 77%) | 94 (57%) (49%, 65%)
Complete Response (%) | 14 (8%) | 8 (5%)
Partial Response (%) | 102 (62%) | 86 (52%)

ORR results were supported by exploratory analyses of patient-reported symptom severity which showed at least a 7-point decrease in the cGVHD Total Symptom Score at any time through Cycle 7 Day 1 in 66 (40%; 95% CI 32, 48) patients in the Jakafi arm and 47 (29%; 95% CI 22, 36) patients in the BAT arm.

16. HOW SUPPLIED/STORAGE AND HANDLING

Jakafi (ruxolitinib) Tablets are available as follows:

Jakafi Trade Presentations
NDC Number | Strength | Description | Tablets per Bottle
50881-005-60 | 5 mg | Round tablet with “INCY” on one side and “5” on the other | 60
50881-010-60 | 10 mg | Round tablet with “INCY” on one side and “10” on the other | 60
50881-015-60 | 15 mg | Oval tablet with “INCY” on one side and “15” on the other | 60
50881-020-60 | 20 mg | Capsule-shaped tablet with “INCY” on one side and “20” on the other | 60
50881-025-60 | 25 mg | Oval tablet with “INCY” on one side and “25” on the other | 60
Store at room temperature 20°C to 25°C (68°F to 77°F); excursions permitted between 15°C and 30°C (59°F and 86°F) [see USP Controlled Room Temperature].

17. PATIENT COUNSELING INFORMATION

Advise the patient to read the FDA-approved patient labeling (Patient Information).

Thrombocytopenia, Anemia and Neutropenia

Inform patients that Jakafi is associated with thrombocytopenia, anemia and neutropenia, and of the need to monitor complete blood counts before and during treatment. Advise patients to observe for and report bleeding [see Warnings and Precautions (5.1)].

Infections

Inform patients of the signs and symptoms of infection and to report any such signs and symptoms promptly.

Inform patients regarding the early signs and symptoms of herpes zoster and of progressive multifocal leukoencephalopathy, and advise patients to seek advice of a clinician if such symptoms are observed [see Warnings and Precautions (5.2)].

Symptom Exacerbation Following Interruption or Discontinuation of Treatment with Jakafi

Inform patients that after discontinuation of treatment, signs and symptoms from myeloproliferative neoplasms are expected to return. Instruct patients not to interrupt or discontinue Jakafi therapy without consulting their physician [see Warnings and Precautions (5.3)].

Non-Melanoma Skin Cancer

Inform patients that Jakafi may increase their risk of certain non-melanoma skin cancers. Advise patients to inform their healthcare provider if they have ever had any type of skin cancer or if they observe any new or changing skin lesions [see Warnings and Precautions (5.4)].

Lipid Elevations

Inform patients that Jakafi may increase blood cholesterol, and of the need to monitor blood cholesterol levels [see Warnings and Precautions (5.5)].

Major Adverse Cardiovascular Events (MACE)

Advise patients that events of major adverse cardiovascular events (MACE) including myocardial infarction, stroke, and cardiovascular death, have been reported in clinical studies with another JAK-inhibitor used to treat rheumatoid arthritis, a condition for which Jakafi is not indicated. Advise patients, especially current or past smokers or patients with other cardiovascular risk factors, to be alert for the development of signs and symptoms of cardiovascular events [see Warnings and Precautions (5.6)].

Thrombosis

Advise patients that events of DVT and PE have been reported in clinical studies with another JAK-inhibitor used to treat rheumatoid arthritis, a condition for which Jakafi is not indicated. Advise patients to tell their healthcare provider if they develop any signs or symptoms of a DVT or PE [see Warnings and Precautions (5.7)].

Secondary Malignancies

Advise patients, especially current or past smokers and patients with a known secondary malignancy (other than a successfully treated NMSC), that lymphoma and other malignancies (excluding NMSC) have been reported in clinical studies with another JAK-inhibitor used to treat rheumatoid arthritis, a condition for which Jakafi is not indicated [see Warnings and Precautions (5.8)].

Drug-Drug Interactions

Advise patients to inform their healthcare providers of all medications they are taking, including over-the-counter medications, herbal products and dietary supplements [see Drug Interactions (7.1) and Clinical Pharmacology (12.3)].

Dialysis

Inform patients on dialysis that their dose should not be taken before dialysis but only following dialysis [see Dosage and Administration (2.7)].

Lactation

Inform women not to breastfeed during treatment with Jakafi and for two weeks after the final dose [see Use in Specific Populations (8.2)].

Compliance

Advise patients to continue taking Jakafi every day for as long as their physician tells them and that this is a long-term treatment. Patients should not change dose or stop taking Jakafi without first consulting their physician. Patients should be aware that after discontinuation of treatment, signs and symptoms from myeloproliferative neoplasms are expected to return.

Manufactured for:
Incyte Corporation
1801 Augustine Cut-off
Wilmington, DE 19803

Jakafi is a registered trademark of Incyte. All rights reserved.
U.S. Patent Nos. 7598257; 8415362; 8722693; 8822481; 8829013; 9079912; 9814722; 10016429
© 2011-2023 Incyte Corporation. All rights reserved.

Patient Information
JAKAFI® (JAK-ah-fye)
(ruxolitinib)
tablets

What is Jakafi?

Jakafi is a prescription medicine used to treat:

- adults with certain types of myelofibrosis (MF).
- adults with polycythemia vera (PV) who have already taken a medicine called hydroxyurea and it did not work well enough or they could not tolerate it.
- adults and children 12 years of age and older with acute graft-versus-host-disease (aGVHD) who have taken corticosteroids and they did not work well enough.
- adults and children 12 years of age and older with chronic graft-versus-host-disease (cGVHD) who have taken one or two types of treatments and they did not work well enough.

It is not known if Jakafi is safe or effective in children for treatment of myelofibrosis or polycythemia vera.

Before taking Jakafi, tell your healthcare provider about of your medical conditions, including if you:

- have an infection
- have or have had low white or red blood cell counts
- have or had tuberculosis (TB), or have been in close contact with someone who has TB
- have had shingles (herpes zoster)
- have or had hepatitis B
- have or have had liver problems
- have or have had kidney problems or are on dialysis. If you are on dialysis, Jakafi should be taken after your dialysis.
- have a high level of fat in your blood (high blood cholesterol or triglycerides)
- have had cancer in the past
- are a current or past smoker
- have had a blood clot, heart attack, other heart problems or stroke
- are pregnant or plan to become pregnant. It is not known if Jakafi will harm your unborn baby.
- are breastfeeding or plan to breastfeed. It is not known if Jakafi passes into your breast milk. Do not breastfeed during treatment with Jakafi and for 2 weeks after the final dose.

Tell your healthcare provider about all the medicines you take, including prescription and over-the-counter medicines, vitamins and herbal supplements. Taking Jakafi with certain other medicines may affect how Jakafi works. Know the medicines you take. Keep a list of them to show your healthcare provider and pharmacist when you get a new medicine.

How should I take Jakafi?

- Take Jakafi exactly as your healthcare provider tells you.
- Do not change your dose or stop taking Jakafi without first talking to your healthcare provider.
- You can take Jakafi with or without food.
- Jakafi may also be given through certain nasogastric tubes.
  - Tell your healthcare provider if you cannot take Jakafi by mouth. Your healthcare provider will decide if you can take Jakafi through a nasogastric tube.
  - Ask your healthcare provider to give you specific instruction on how to properly take Jakafi through a nasogastric tube.
- If you miss a dose of Jakafi, take your next dose at your regular time. Do not take 2 doses at the same time.
- If you take too much Jakafi call your healthcare provider or go to the nearest hospital emergency room right away.
- You will have regular blood tests during your treatment with Jakafi. Your healthcare provider may change your dose of Jakafi or stop your treatment based on the results of your blood tests.

What are the possible side effects of Jakafi?
Jakafi can cause serious side effects including:
Low blood cell counts. Jakafi may cause low platelet counts (thrombocytopenia), low red blood cell counts (anemia), and low white blood cell counts (neutropenia). If you develop bleeding, stop Jakafi and call your healthcare provider. Your healthcare provider will do a blood test to check your blood cell counts before you start Jakafi and regularly during your treatment with Jakafi. Tell your healthcare provider right away if you develop or have worsening of any of these symptoms:

- unusual bleeding
- bruising
- tiredness

- shortness of breath
- fever

Infection. You may be at risk for developing a serious infection during treatment with Jakafi. Tell your healthcare provider if you develop any of the following symptoms of infection:

- chills
- aches
- fever
- nausea

- vomiting
- weakness
- painful skin rash or blisters

Cancer. Some people have had certain types of non-melanoma skin cancers during treatment with Jakafi. Your healthcare provider will regularly check your skin during your treatment with Jakafi. Tell your healthcare provider if you develop any new or changing skin lesions during treatment with Jakafi.

Cholesterol increases. You may have changes in your blood cholesterol levels during treatment with Jakafi. Your healthcare provider will do blood tests to check your cholesterol levels about every 8 to 12 weeks after you start taking Jakafi, and as needed.

Increased risk of major cardiovascular events such as heart attack, stroke or death in people who have cardiovascular risk factors and who are current or past smokers while using another JAK inhibitor to treat rheumatoid arthritis.

Get emergency help right away if you have any symptoms of a heart attack or stroke while taking Jakafi, including:

- discomfort in the center of your chest that lasts for more than a few minutes, or that goes away and comes back
- severe tightness, pain, pressure, or heaviness in your chest, throat, neck, or jaw
- pain or discomfort in your arms, back, neck, jaw, or stomach
- shortness of breath with or without chest discomfort
- breaking out in a cold sweat
- nausea or vomiting
- feeling lightheaded
- weakness in one part or on one side of your body
- slurred speech

Increased risk of blood clots. Blood clots in the veins of your legs (deep vein thrombosis, DVT) or lungs (pulmonary embolism, PE) have happened in people taking another JAK inhibitor for rheumatoid arthritis and may be life-threatening.

- Tell your healthcare provider right away if you have any signs and symptoms of blood clots during treatment with Jakafi, including:
  º swelling, pain or tenderness in one or both legs
  º sudden, unexplained chest or upper back pain
  º shortness of breath or difficulty breathing

Possible increased risk of new (secondary) cancers. People who take another JAK inhibitor for rheumatoid arthritis have an increased risk of new (secondary) cancers, including lymphoma and other cancers. People who smoke or who smoked in the past have an added risk of new cancers.

The most common side effects of Jakafi in adults with certain types of MF and PV include:

- low platelet counts
- low red blood cell counts
- bruising

- dizziness
- headache
- diarrhea

The most common side effects of Jakafi in people with aGVHD include:

- low red blood cell counts
- low platelet counts
- low white blood cell counts

- infections
- swelling

The most common side effects of Jakafi in people with cGVHD include:

- low red blood cell counts
- low platelet counts

- infections, including viral infections

These are not all of the possible side effects of Jakafi.
Call your doctor for medical advice about side effects. You may report side effects to FDA at 1-800-FDA-1088.
You may also report side effects to Incyte Corporation at 1-855-463-3463.

How should I store Jakafi?

- Store Jakafi at room temperature 68°F to 77°F (20°C to 25°C).

Keep Jakafi and all medicines out of the reach of children.

General information about the safe and effective use of Jakafi.
Medicines are sometimes prescribed for purposes other than those listed in Patient Information. Do not use Jakafi for a condition for which it is not prescribed. Do not give Jakafi to other people, even if they have the same symptoms you have. It may harm them. You can ask your pharmacist or healthcare provider for information that is written for healthcare professionals.

What are the ingredients in Jakafi?
Active ingredient: ruxolitinib phosphate
Inactive ingredients: microcrystalline cellulose, lactose monohydrate, magnesium stearate, colloidal silicon dioxide, sodium starch glycolate, povidone and hydroxypropyl cellulose
Manufactured for: Incyte Corporation, 1801 Augustine Cut-off, Wilmington, DE 19803
Jakafi is a registered trademark of Incyte. All rights reserved.
U.S. Patent Nos. 7598257; 8415362; 8722693; 8822481; 8829013; 9079912; 9814722; 10016429
© 2011-2021 Incyte Corporation. All rights reserved.
For more information call 1-855-463-3463 or go to www.jakafi.com.

This Patient Information has been approved by the U.S. Food and Drug Administration. Revised: September 2021

5 mg Tablet Bottle Label

Rx only

NDC 50881-005-60

Jakafi® (Ruxolitinib) Tablets

5 mg

60 tablets

Each tablet contains 6.6 mg ruxolitinib phosphate equivalent to 5 mg ruxolitinib free base.

10 mg Tablet Bottle Label

Rx only

NDC 50881-010-60

Jakafi® (Ruxolitinib) Tablets

10 mg

60 tablets

Each tablet contains 13.2 mg ruxolitinib phosphate equivalent to 10 mg ruxolitinib free base.

15 mg Tablet Bottle Label

Rx only

NDC 50881-015-60

Jakafi® (Ruxolitinib) Tablets

15 mg

60 tablets

Each tablet contains 19.8 mg ruxolitinib phosphate equivalent to 15 mg ruxolitinib free base.

20 mg Tablet Bottle Label

Rx only

NDC 50881-020-60

Jakafi® (Ruxolitinib) Tablets

20 mg

60 tablets

Each tablet contains 26.4 mg ruxolitinib phosphate equivalent to 20 mg ruxolitinib free base.

25 mg Tablet Bottle Label

Rx only

NDC 50881-025-60

Jakafi® (Ruxolitinib) Tablets

25 mg

60 tablets

Each tablet contains 33 mg ruxolitinib phosphate equivalent to 25 mg ruxolitinib free base.